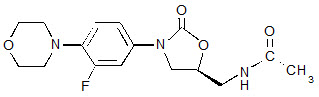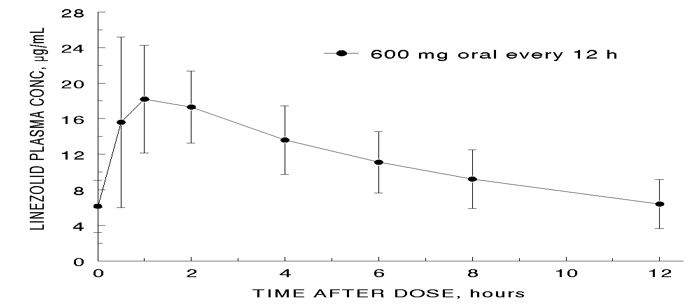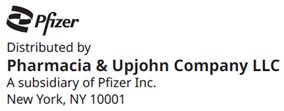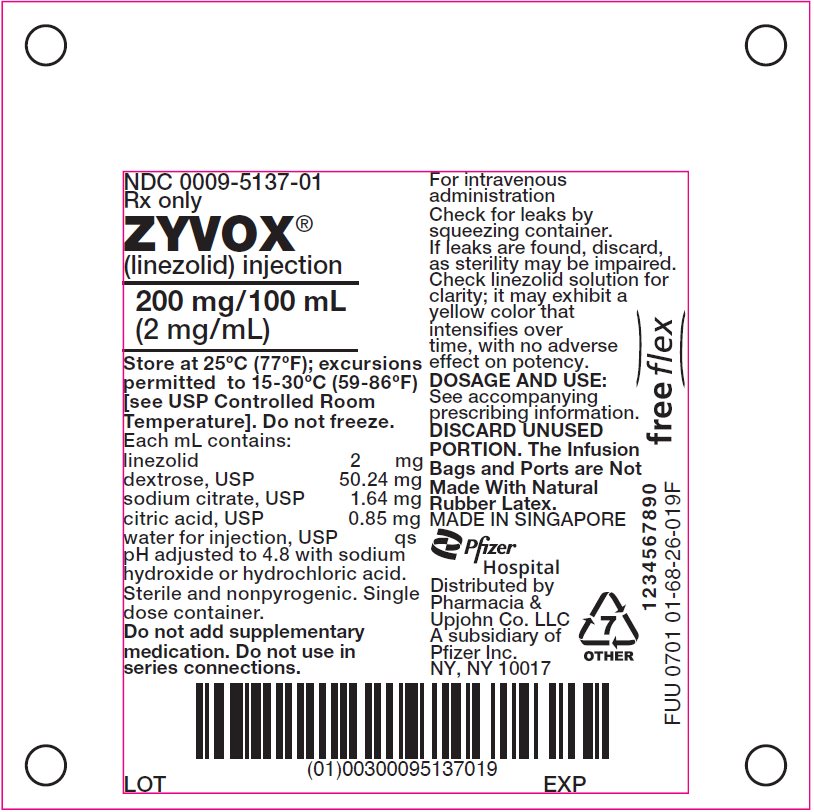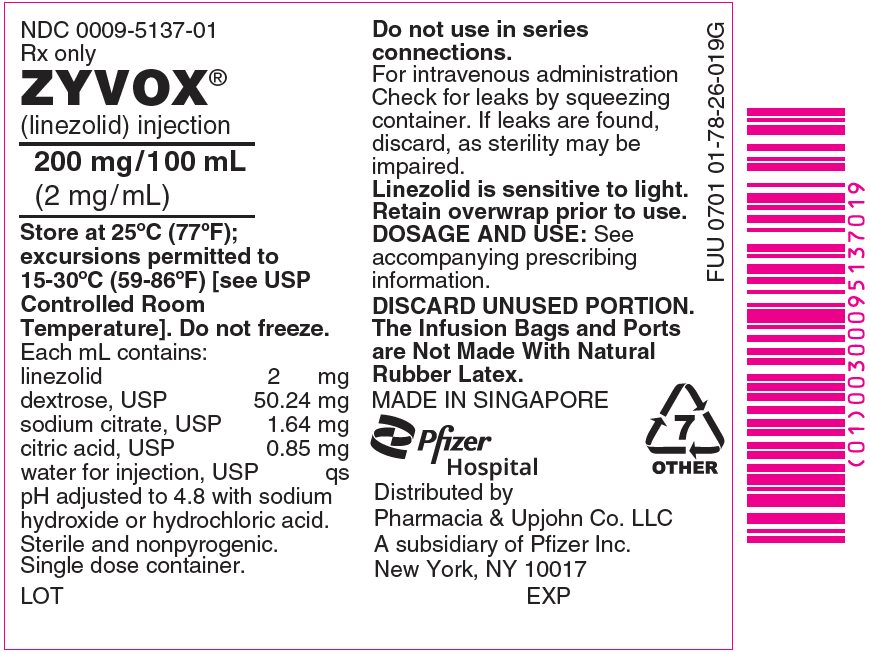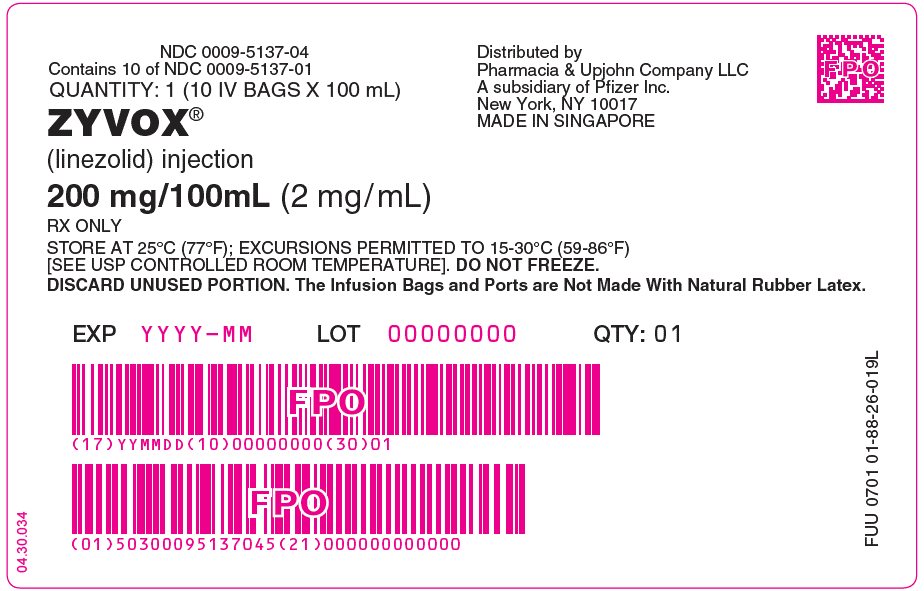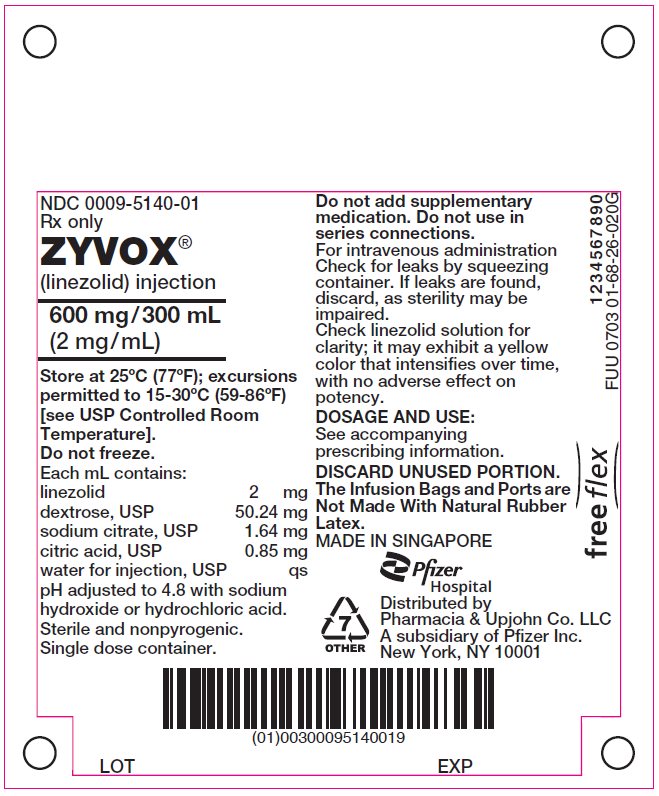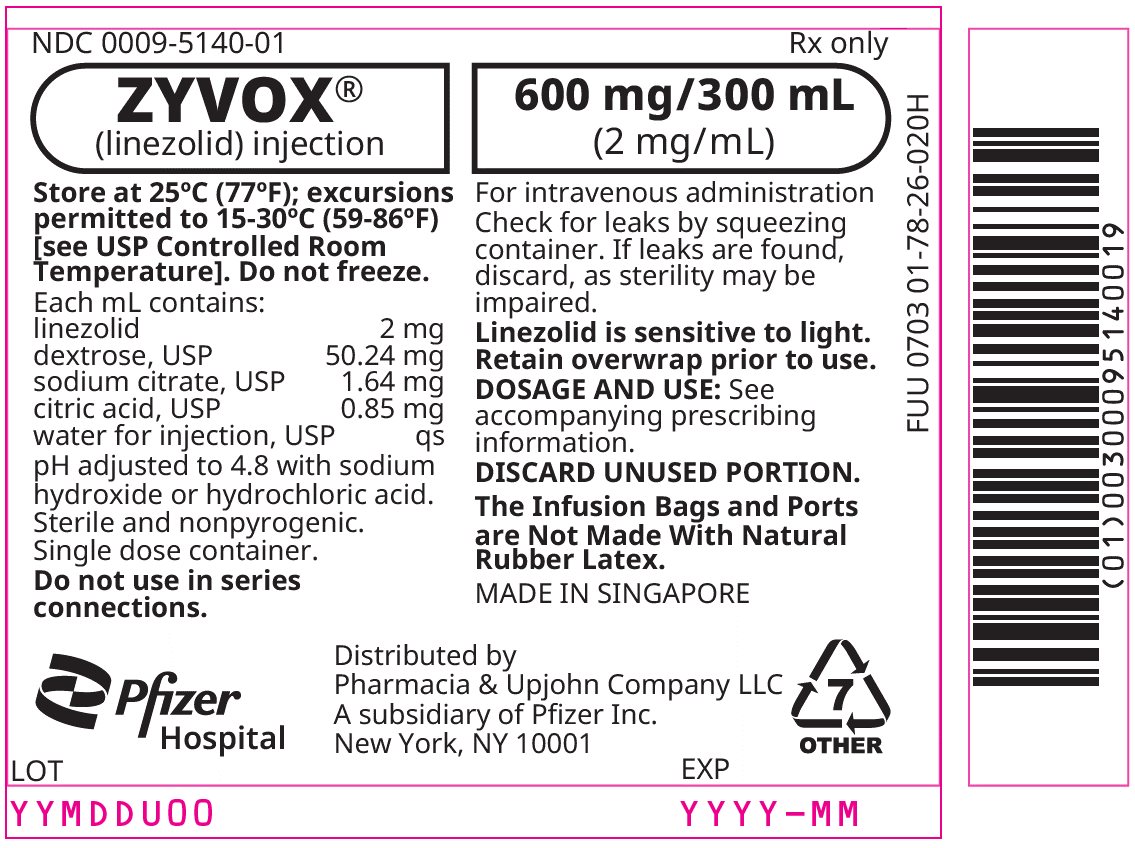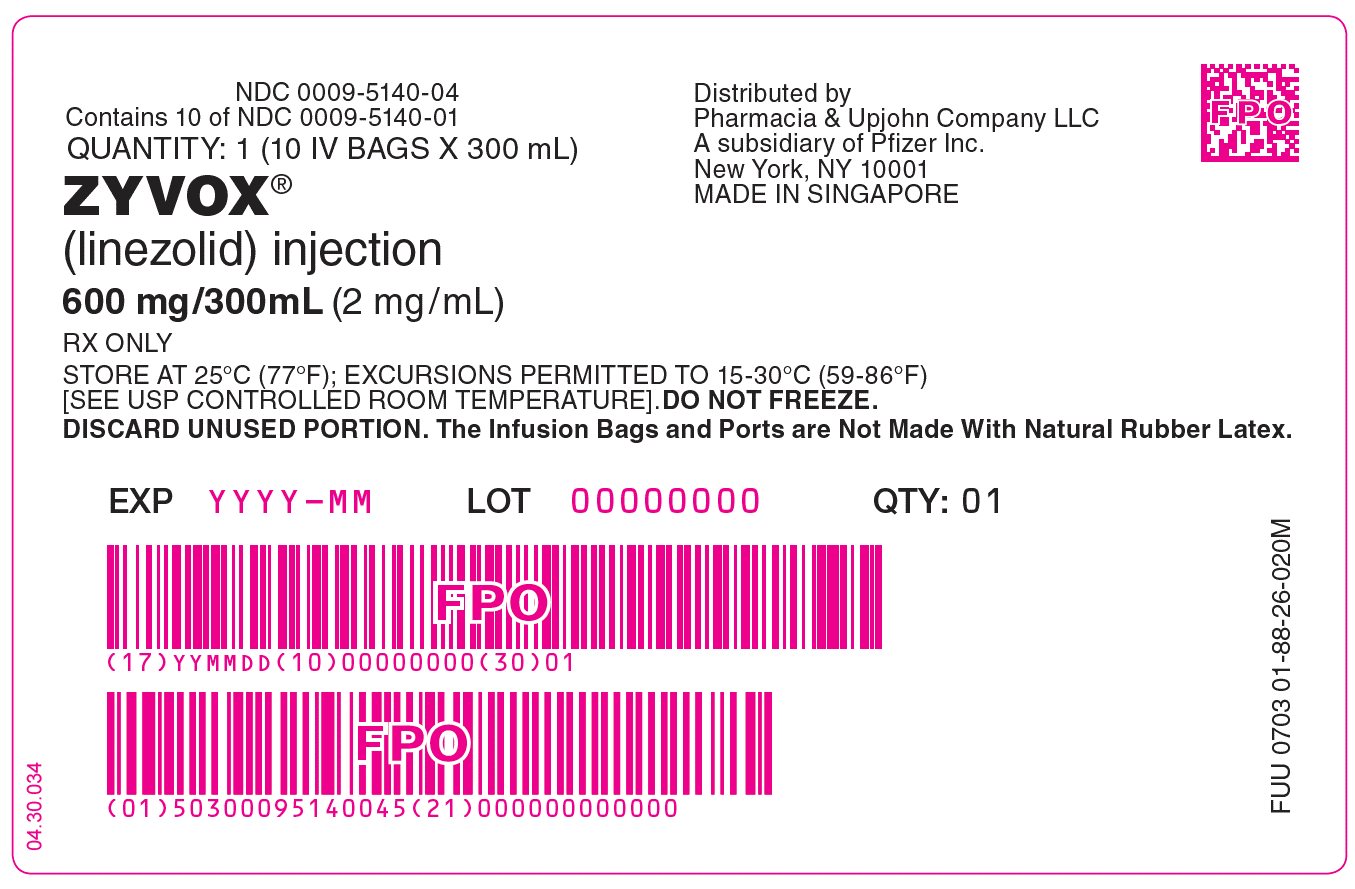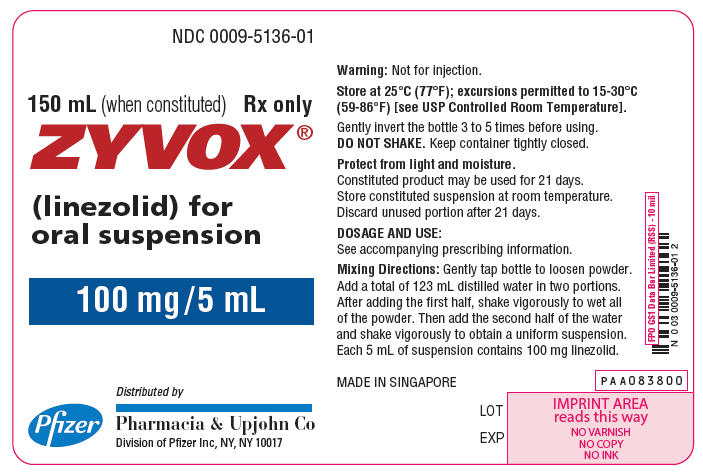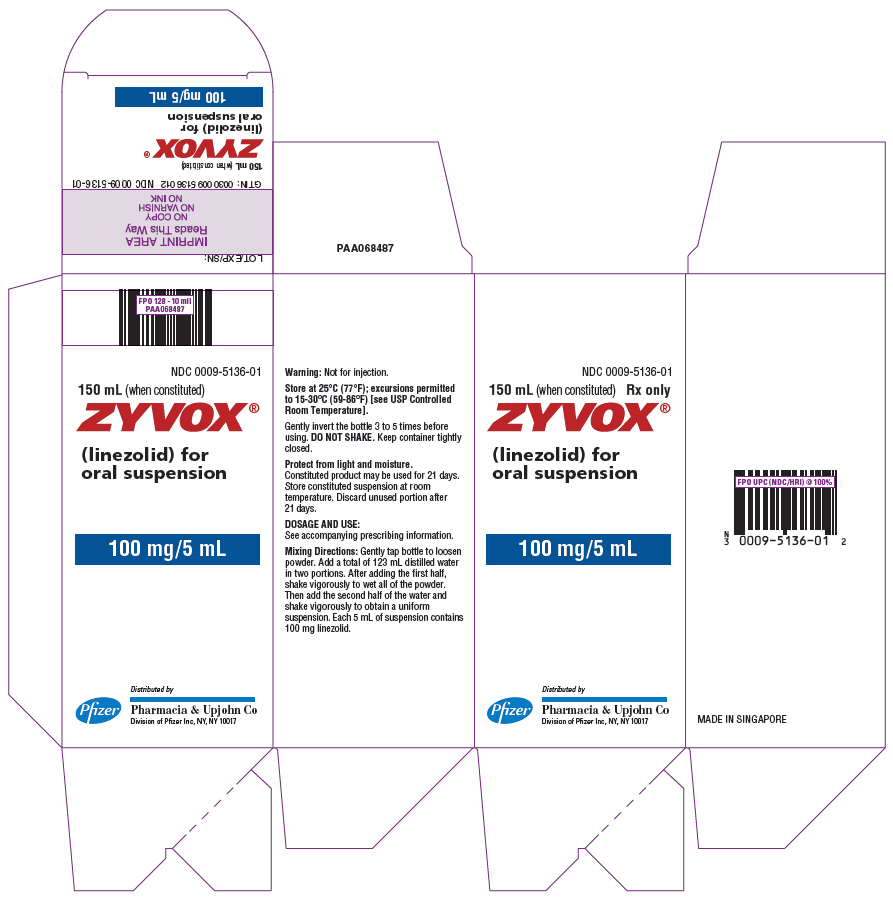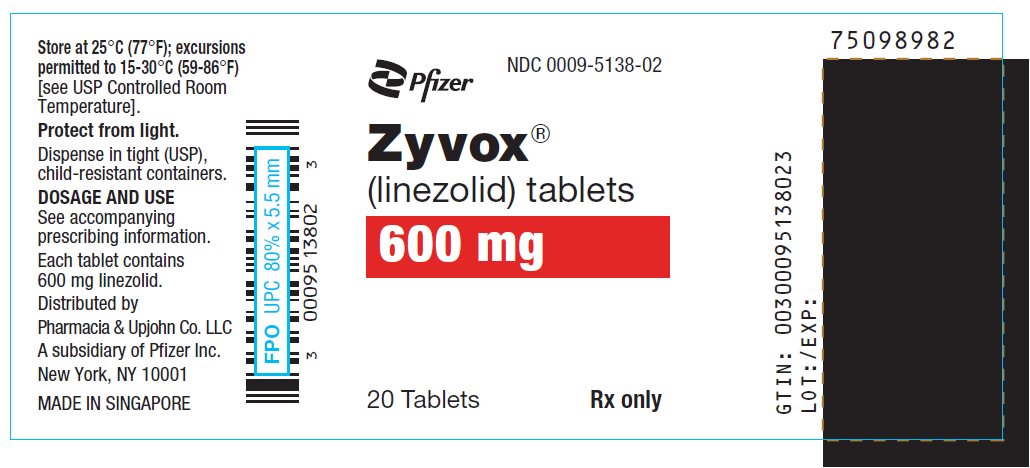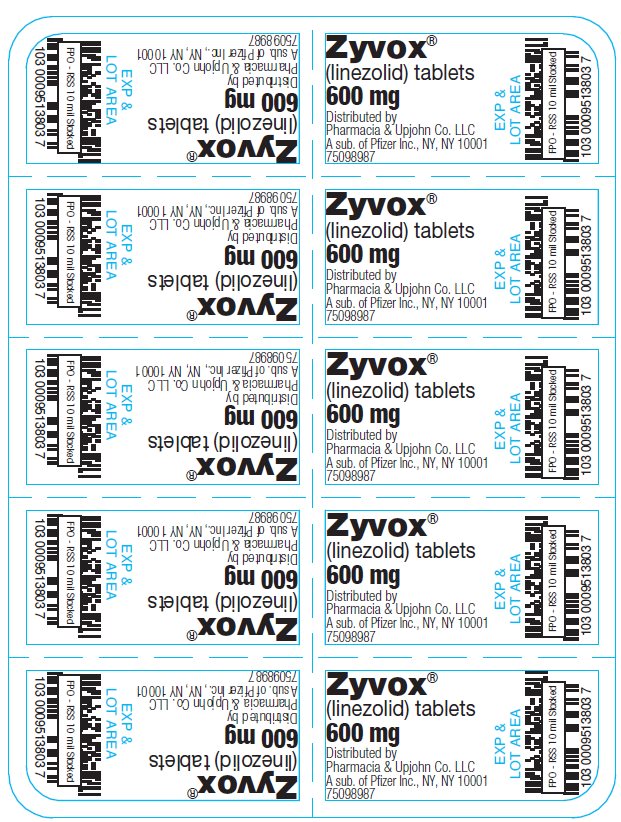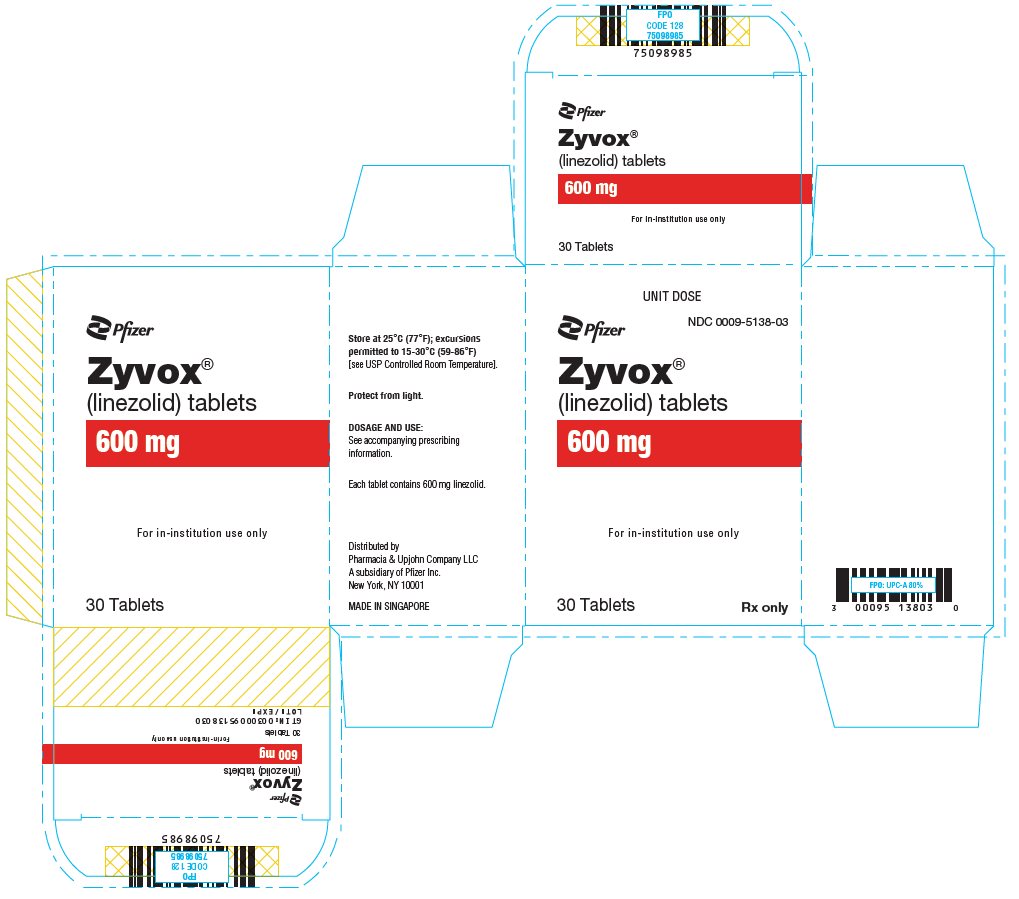 DRUG LABEL: Zyvox
NDC: 0009-5137 | Form: INJECTION, SOLUTION
Manufacturer: Pharmacia & Upjohn Company LLC
Category: prescription | Type: HUMAN PRESCRIPTION DRUG LABEL
Date: 20260123

ACTIVE INGREDIENTS: LINEZOLID 200 mg/100 mL
INACTIVE INGREDIENTS: TRISODIUM CITRATE DIHYDRATE; ANHYDROUS CITRIC ACID; DEXTROSE MONOHYDRATE; HYDROCHLORIC ACID; SODIUM HYDROXIDE

HIGHLIGHTS OF PRESCRIBING INFORMATION

These highlights do not include all the information needed to use ZYVOX safely and effectively. See full prescribing information for ZYVOX.
ZYVOX® (linezolid) injection, for intravenous use
ZYVOX® (linezolid) tablets, for oral use
ZYVOX® (linezolid) for oral suspension
Initial U.S. Approval: 2000

RECENT MAJOR CHANGES

Warnings and Precautions, Myelosuppression (5.1) | 7/2023
Warnings and Precautions, Rhabdomyolysis (5.9) | 6/2024

1 INDICATIONS AND USAGE

ZYVOX is an oxazolidinone-class antibacterial indicated in adults and children for the treatment of the following infections caused by susceptible Gram-positive bacteria: Nosocomial pneumonia (1.1); Community-acquired pneumonia (1.2); Complicated skin and skin structure infections, including diabetic foot infections, without concomitant osteomyelitis (1.3); Uncomplicated skin and skin structure infections (1.4); Vancomycin-resistant Enterococcus faecium infections. (1.5)

Limitations of Use (1.6):

- ZYVOX is not indicated for the treatment of Gram-negative infections.
- The safety and efficacy of ZYVOX formulations given for longer than 28 days have not been evaluated in controlled clinical trials.

To reduce the development of drug-resistant bacteria and maintain the effectiveness of ZYVOX formulations and other antibacterial drugs, ZYVOX should be used only to treat or prevent infections that are proven or strongly suspected to be caused by bacteria. (1.7)

2 DOSAGE AND ADMINISTRATION

 | Dosage, Route, and Frequency of Administration
Infection | Pediatric Patients (Birth through 11 years of Age) | Adults and Adolescents (12 years and Older) | Duration (days)
Nosocomial pneumonia | 10 mg/kg intravenous or oral every 8 hours | 600 mg intravenous or oral every 12 hours | 10 to 14
Community-acquired pneumonia, including concurrent bacteremia | 10 mg/kg intravenous or oral every 8 hours | 600 mg intravenous or oral every 12 hours | 10 to 14
Complicated skin and skin structure infections | 10 mg/kg intravenous or oral every 8 hours | 600 mg intravenous or oral every 12 hours | 10 to 14
Vancomycin-resistant Enterococcus faecium infections, including concurrent bacteremia | 10 mg/kg intravenous or oral every 8 hours | 600 mg intravenous or oral every 12 hours | 14 to 28
Uncomplicated skin and skin structure infections | less than 5 yrs: 10 mg/kg oral every 8 hours 5–11 yrs: 10 mg/kg oral every 12 hours | Adults: 400 mg oral every 12 hours Adolescents: 600 mg oral every 12 hours | 10 to 14

3 DOSAGE FORMS AND STRENGTHS

- Injection: 200 mg/100 mL (2 mg/mL) and 600 mg/300 mL (2 mg/mL) linezolid. (3)
- Tablet: 600 mg linezolid. (3)
- For oral suspension: 100 mg of linezolid per each 5 mL. (3)

4 CONTRAINDICATIONS

- Known hypersensitivity to linezolid or any of the other product components. (4.1)
- Patients taking any monoamine oxidase inhibitors (MAOI) or within two weeks of taking an MAOI. (4.2)

5 WARNINGS AND PRECAUTIONS

- Myelosuppression: Monitor complete blood counts weekly. Thrombocytopenia has been reported more often in patients with severe renal and in patients with moderate to severe hepatic impairment. Consider discontinuation in patients who develop or have worsening myelosuppression. (5.1)
- Peripheral and Optic Neuropathy: Reported primarily in patients treated for longer than 28 days. If patients experience symptoms of visual impairment, prompt ophthalmic evaluation is recommended. (5.2)
- Serotonin Syndrome: Monitor patients taking serotonergic agents, including antidepressants and opioids, for signs of serotonin syndrome. Patients taking serotonergic antidepressants should receive ZYVOX only if no other therapies are available. Discontinue serotonergic antidepressants and monitor patients for signs and symptoms of both serotonin syndrome and antidepressant discontinuation. (5.3)
- A mortality imbalance was seen in an investigational study in linezolid-treated patients with catheter-related bloodstream infections. (5.4)
- Clostridioides difficile-Associated Diarrhea: Evaluate if diarrhea occurs. (5.5)
- Potential interactions producing elevation of blood pressure: monitor blood pressure. (5.6)
- Rhabdomyolysis: If signs or symptoms of rhabdomyolysis are observed, discontinue ZYVOX and initiate appropriate therapy. (5.9)
- Hypoglycemia: Postmarketing cases of symptomatic hypoglycemia have been reported in patients with diabetes mellitus receiving insulin or oral hypoglycemic agents. (5.10)
- Hyponatremia and/or Syndrome of Inappropriate Antidiuretic Hormone Secretion (SIADH): Monitor serum sodium levels regularly in patients at risk of hyponatremia and/or SIADH. (5.11)
- Phenylketonuria: ZYVOX for Oral Suspension contains phenylalanine which can be harmful to patients with phenylketonuria. (5.12)

6 ADVERSE REACTIONS

Most common adverse reactions (>5% of adult and/or pediatric patients treated with ZYVOX) include: diarrhea, vomiting, headache, nausea, and anemia. (6)
To report SUSPECTED ADVERSE REACTIONS, contact Pfizer Inc. at 1-800-438-1985 or FDA at 1-800-FDA-1088 or www.fda.gov/medwatch.

7 DRUG INTERACTIONS

Monoamine oxidase inhibitors and potential for interaction with adrenergic and serotonergic agents. (4.2, 5.3, 5.6, 7, 12.3)

FULL PRESCRIBING INFORMATION

1 INDICATIONS AND USAGE

1.1 Nosocomial Pneumonia

ZYVOX is indicated for the treatment of nosocomial pneumonia caused by Staphylococcus aureus (methicillin-susceptible and -resistant isolates) or Streptococcus pneumoniae [see Clinical Studies (14)].

1.2 Community-acquired Pneumonia

ZYVOX is indicated for the treatment of community-acquired pneumonia caused by Streptococcus pneumoniae, including cases with concurrent bacteremia, or Staphylococcus aureus (methicillin-susceptible isolates only) [see Clinical Studies (14)].

1.3 Complicated Skin and Skin Structure Infections

ZYVOX is indicated for the treatment of complicated skin and skin structure infections, including diabetic foot infections, without concomitant osteomyelitis, caused by Staphylococcus aureus (methicillin-susceptible and -resistant isolates), Streptococcus pyogenes, or Streptococcus agalactiae. ZYVOX has not been studied in the treatment of decubitus ulcers [see Clinical Studies (14)].

1.4 Uncomplicated Skin and Skin Structure Infections

ZYVOX is indicated for the treatment of uncomplicated skin and skin structure infections caused by Staphylococcus aureus (methicillin-susceptible isolates only) or Streptococcus pyogenes [see Clinical Studies (14)].

1.5 Vancomycin-resistant Enterococcus faecium Infections

ZYVOX is indicated for the treatment of vancomycin-resistant Enterococcus faecium infections, including cases with concurrent bacteremia [see Clinical Studies (14)].

1.6 Limitations of Use

- ZYVOX is not indicated for the treatment of Gram-negative infections. It is critical that specific Gram-negative therapy be initiated immediately if a concomitant Gram-negative pathogen is documented or suspected [see Warnings and Precautions (5.4)].
- The safety and efficacy of ZYVOX formulations given for longer than 28 days have not been evaluated in controlled clinical trials [see Clinical Studies (14)].

1.7 Usage

To reduce the development of drug-resistant bacteria and maintain the effectiveness of ZYVOX and other antibacterial drugs, ZYVOX should be used only to treat or prevent infections that are proven or strongly suspected to be caused by susceptible bacteria. When culture and susceptibility information are available, they should be considered in selecting or modifying antibacterial therapy. In the absence of such data, local epidemiology and susceptibility patterns may contribute to the empiric selection of therapy.

2 DOSAGE AND ADMINISTRATION

2.1 General Dosage and Administration

The recommended dosage for ZYVOX formulations for the treatment of infections is described in Table 1.

Table 1. Dosage Guidelines for ZYVOX
 | Dosage, Route and Frequency of Administration |  | Recommended Duration of Treatment (consecutive days)
Infection [Due to the designated pathogens [see Indications and Usage (1)]] | Pediatric Patients [Neonates less than 7 days: Most pre-term neonates less than 7 days of age (gestational age less than 34 weeks) have lower systemic linezolid clearance values and larger AUC values than many full-term neonates and older infants. These neonates should be initiated with a dosing regimen of 10 mg/kg every 12 hours. Consideration may be given to the use of 10 mg/kg every 8 hours regimen in neonates with a sub-optimal clinical response. All neonatal patients should receive 10 mg/kg every 8 hours by 7 days of life [see Use in Specific Populations (8.4) and Clinical Pharmacology (12.3)].] (Birth through 11 Years of Age) | Adults and Adolescents (12 Years and Older) | Recommended Duration of Treatment (consecutive days)
Nosocomial pneumonia | 10 mg/kg intravenously or oral [Oral dosing using either ZYVOX Tablets or ZYVOX for Oral Suspension [see How Supplied/Storage and Handling (16)].] every 8 hours | 600 mg intravenously or oral every 12 hours | 10 to 14
Community-acquired pneumonia, including concurrent bacteremia | 10 mg/kg intravenously or oral [Oral dosing using either ZYVOX Tablets or ZYVOX for Oral Suspension [see How Supplied/Storage and Handling (16)].] every 8 hours | 600 mg intravenously or oral every 12 hours | 10 to 14
Complicated skin and skin structure infections | 10 mg/kg intravenously or oral [Oral dosing using either ZYVOX Tablets or ZYVOX for Oral Suspension [see How Supplied/Storage and Handling (16)].] every 8 hours | 600 mg intravenously or oral every 12 hours | 10 to 14
Vancomycin-resistant Enterococcus faecium infections, including concurrent bacteremia | 10 mg/kg intravenously or oral every 8 hours | 600 mg intravenously or oral every 12 hours | 14 to 28
Uncomplicated skin and skin structure infections | less than 5 yrs: 10 mg/kg oral every 8 hours 5–11 yrs: 10 mg/kg oral every 12 hours | Adults: 400 mg oral every 12 hours Adolescents: 600 mg oral every 12 hours | 10 to 14

No dose adjustment is necessary when switching from intravenous to oral administration.

2.2 Intravenous Administration

ZYVOX I.V. Injection is supplied in single-dose, ready-to-use infusion bags. Parenteral drug products should be inspected visually for particulate matter prior to administration. Check for minute leaks by firmly squeezing the bag. If leaks are detected, discard the solution, as sterility may be impaired. Keep the infusion bags in the overwrap until ready to use. Store at room temperature. Protect from freezing. ZYVOX I.V. Injection may exhibit a yellow color that can intensify over time without adversely affecting potency.

ZYVOX I.V. Injection should be administered by intravenous infusion over a period of 30 to 120 minutes. Do not use this intravenous infusion bag in series connections. Additives should not be introduced into this solution. If ZYVOX I.V. Injection is to be given concomitantly with another drug, each drug should be given separately in accordance with the recommended dosage and route of administration for each product. Discard unused portion.

If the same intravenous line is used for sequential infusion of several drugs, the line should be flushed before and after infusion of ZYVOX I.V. Injection with an infusion solution compatible with ZYVOX I.V. Injection and with any other drug(s) administered via this common line.

2.3 Compatibilities

Compatible intravenous solutions include 0.9% Sodium Chloride Injection, USP, 5% Dextrose Injection, USP, and Lactated Ringer's Injection, USP.

2.4 Incompatibilities

Physical incompatibilities resulted when ZYVOX I.V. Injection was combined with the following drugs during simulated Y-site administration: amphotericin B, chlorpromazine HCl, diazepam, pentamidine isothionate, erythromycin lactobionate, phenytoin sodium, and trimethoprim-sulfamethoxazole. Additionally, chemical incompatibility resulted when ZYVOX I.V. Injection was combined with ceftriaxone sodium.

2.5 Constitution of Oral Suspension

ZYVOX for Oral Suspension is supplied as a powder/granule for constitution. Gently tap bottle to loosen powder. Add a total of 123 mL distilled water in two portions. After adding the first half, shake vigorously to wet all of the powder. Then add the second half of the water and shake vigorously to obtain a uniform suspension. After constitution, each 5 mL of the suspension contains 100 mg of linezolid. Before using, gently mix by inverting the bottle 3 to 5 times. Do not shake. Store constituted suspension at room temperature. Use within 21 days after constitution.

3 DOSAGE FORMS AND STRENGTHS

ZYVOX I.V. Injection: 200 mg/100 mL (2 mg/mL) and 600 mg/300 mL (2 mg/mL) linezolid single-dose, ready-to-use flexible plastic infusion bags in a foil laminate overwrap.

ZYVOX 600 mg Tablet:

white, capsule-shaped, film-coated tablet debossed with "ZYV" on one side and "600" on the other

ZYVOX for Oral Suspension: dry, white to off-white, orange-flavored granule/powder. When constituted as directed, each bottle will contain 150 mL of a suspension providing the equivalent of 100 mg of linezolid per each 5 mL.

4 CONTRAINDICATIONS

4.1 Hypersensitivity

ZYVOX formulations are contraindicated for use in patients who have known hypersensitivity to linezolid or any of the other product components.

4.2 Monoamine Oxidase Inhibitors

Linezolid should not be used in patients taking any medicinal product which inhibits monoamine oxidases A or B (e.g., phenelzine, isocarboxazid) or within two weeks of taking any such medicinal product.

5 WARNINGS AND PRECAUTIONS

5.1 Myelosuppression

Myelosuppression (including anemia, leukopenia, pancytopenia, and thrombocytopenia) has been reported in patients receiving linezolid. In cases where the outcome is known, when linezolid was discontinued, the affected hematologic parameters have risen toward pretreatment levels. Thrombocytopenia has been reported more often in patients with severe renal impairment, whether or not on dialysis, and in patients with moderate to severe hepatic impairment. Complete blood counts should be monitored weekly in patients who receive linezolid, particularly in those who receive linezolid for longer than two weeks, those with pre-existing myelosuppression, those with severe renal impairment or moderate to severe hepatic impairment, those receiving concomitant drugs that produce bone marrow suppression, or those with a chronic infection who have received previous or concomitant antibacterial drug therapy. Discontinuation of therapy with linezolid should be considered in patients who develop or have worsening myelosuppression [see Adverse Reactions (6.2)].

5.2 Peripheral and Optic Neuropathy

Peripheral and optic neuropathies have been reported in patients treated with ZYVOX, primarily in those patients treated for longer than the maximum recommended duration of 28 days. In cases of optic neuropathy that progressed to loss of vision, patients were treated for extended periods beyond the maximum recommended duration. Visual blurring has been reported in some patients treated with ZYVOX for less than 28 days. Peripheral and optic neuropathy has also been reported in children.

If patients experience symptoms of visual impairment, such as changes in visual acuity, changes in color vision, blurred vision, or visual field defect, prompt ophthalmic evaluation is recommended. Visual function should be monitored in all patients taking ZYVOX for extended periods (≥ 3 months) and in all patients reporting new visual symptoms regardless of length of therapy with ZYVOX. If peripheral or optic neuropathy occurs, the continued use of ZYVOX in these patients should be weighed against the potential risks.

5.3 Serotonin Syndrome

Spontaneous reports of serotonin syndrome including fatal cases associated with the co-administration of ZYVOX and serotonergic agents, including antidepressants such as selective serotonin reuptake inhibitors (SSRIs), have been reported.

Unless clinically appropriate and patients are carefully observed for signs and/or symptoms of serotonin syndrome or neuroleptic malignant syndrome-like (NMS-like) reactions, linezolid should not be administered to patients with carcinoid syndrome and/or patients taking any of the following medications: serotonin re-uptake inhibitors, tricyclic antidepressants, bupropion, buspirone, serotonin 5-HT1 receptor agonists (triptans), and opioids, including meperidine [see Drug Interactions (7) and Clinical Pharmacology (12.3)].

In some cases, a patient already receiving a serotonergic antidepressant or buspirone may require urgent treatment with linezolid. If alternatives to linezolid are not available and the potential benefits of linezolid outweigh the risks of serotonin syndrome or NMS-like reactions, the serotonergic antidepressant should be stopped promptly and linezolid administered. The patient should be monitored for two weeks (five weeks if fluoxetine was taken) or until 24 hours after the last dose of linezolid, whichever comes first. Symptoms of serotonin syndrome or NMS-like reactions include hyperthermia, rigidity, myoclonus, autonomic instability, and mental status changes that include extreme agitation progressing to delirium and coma. The patient should also be monitored for discontinuation symptoms of the antidepressant (see package insert of the specified agent(s) for a description of the associated discontinuation symptoms).

5.4 Mortality Imbalance in an Investigational Study in Patients with Catheter-Related Bloodstream Infections, Including Those with Catheter-site Infections

An imbalance in mortality was seen in patients treated with linezolid relative to vancomycin/dicloxacillin/oxacillin in an open-label study in seriously ill patients with intravascular catheter-related infections [78/363 (21.5%) vs. 58/363 (16.0%); odds ratio 1.426, 95% CI 0.970, 2.098]. While causality has not been established, this observed imbalance occurred primarily in linezolid-treated patients in whom either Gram-negative pathogens, mixed Gram-negative and Gram-positive pathogens, or no pathogen were identified at baseline, but was not seen in patients with Gram-positive infections only.

Linezolid is not approved and should not be used for the treatment of patients with catheter-related bloodstream infections or catheter-site infections.

Linezolid has no clinical activity against Gram-negative pathogens and is not indicated for the treatment of Gram-negative infections. It is critical that specific Gram-negative therapy be initiated immediately if a concomitant Gram-negative pathogen is documented or suspected [see Indications and Usage (1)].

5.5 Clostridioides difficile-Associated Diarrhea

Clostridioides difficile-Associated Diarrhea (CDAD) has been reported with use of nearly all antibacterial agents, including ZYVOX, and may range in severity from mild diarrhea to fatal colitis. Treatment with antibacterial agents alters the normal flora of the colon leading to overgrowth of C. difficile.

C. difficile produces toxins A and B which contribute to the development of CDAD. Hypertoxin producing strains of C. difficile cause increased morbidity and mortality, as these infections can be refractory to antimicrobial therapy and may require colectomy. CDAD must be considered in all patients who present with diarrhea following antibacterial drug use.

Careful medical history is necessary since CDAD has been reported to occur over two months after the administration of antibacterial agents.

If CDAD is suspected or confirmed, ongoing antibacterial drug use not directed against C. difficile may need to be discontinued. Appropriate fluid and electrolyte management, protein supplementation, antibacterial drug treatment of C. difficile, and surgical evaluation should be instituted as clinically indicated.

5.6 Potential Interactions Producing Elevation of Blood Pressure

Unless patients are monitored for potential increases in blood pressure, linezolid should not be administered to patients with uncontrolled hypertension, pheochromocytoma, thyrotoxicosis and/or patients taking any of the following types of medications: directly and indirectly acting sympathomimetic agents (e.g., pseudoephedrine), vasopressive agents (e.g., epinephrine, norepinephrine), dopaminergic agents (e.g., dopamine, dobutamine) [see Drug Interactions (7) and Clinical Pharmacology (12.3)].

5.7 Lactic Acidosis

Lactic acidosis has been reported with the use of ZYVOX. In reported cases, patients experienced repeated episodes of nausea and vomiting. Patients who develop recurrent nausea or vomiting, unexplained acidosis, or a low bicarbonate level while receiving ZYVOX should receive immediate medical evaluation.

5.8 Convulsions

Convulsions have been reported in patients when treated with linezolid. In some of these cases, a history of seizures or risk factors for seizures was reported.

5.9 Rhabdomyolysis

Rhabdomyolysis has been reported with the use of linezolid, including ZYVOX [see Adverse Reactions (6.2)]. If signs or symptoms of rhabdomyolysis such as muscle pain, tenderness or weakness, dark urine or elevated creatine phosphokinase are observed, discontinue ZYVOX and initiate appropriate therapy.

5.10 Hypoglycemia

Postmarketing cases of symptomatic hypoglycemia have been reported in patients with diabetes mellitus receiving insulin or oral hypoglycemic agents when treated with linezolid, a reversible, nonselective MAO inhibitor. Some MAO inhibitors have been associated with hypoglycemic episodes in diabetic patients receiving insulin or hypoglycemic agents. While a causal relationship between linezolid and hypoglycemia has not been established, diabetic patients should be cautioned of potential hypoglycemic reactions when treated with linezolid.

If hypoglycemia occurs, a decrease in the dose of insulin or oral hypoglycemic agent, or discontinuation of oral hypoglycemic agent, insulin, or linezolid may be required.

5.11 Hyponatremia and/or Syndrome of Inappropriate Antidiuretic Hormone Secretion (SIADH)

Postmarketing cases of hyponatremia and/or Syndrome of Inappropriate Antidiuretic Hormone Secretion (SIADH) have been observed in patients treated with linezolid. In reported cases, the signs and symptoms included confusion, somnolence, generalized weakness, and in severe cases led to respiratory failure and even death. Monitor serum sodium levels regularly in the elderly, in patients taking diuretics, and in other patients at risk of hyponatremia and/or SIADH while taking ZYVOX. If signs and symptoms of hyponatremia and/or SIADH occur, discontinue ZYVOX, and institute appropriate supportive measures.

5.12 Risks in Patients with Phenylketonuria

Phenylalanine can be harmful to patients with phenylketonuria (PKU). ZYVOX for Oral Suspension contains phenylalanine, a component of aspartame. Each 5 mL of the 100 mg/5 mL oral suspension contains 20 mg of phenylalanine. Before prescribing ZYVOX for Oral Suspension to a patient with PKU, consider the combined daily amount of phenylalanine from all sources, including ZYVOX for Oral Suspension.

The other ZYVOX formulations do not contain phenylalanine.

5.13 Development of Drug-Resistant Bacteria

Prescribing ZYVOX in the absence of a proven or strongly suspected bacterial infection or a prophylactic indication is unlikely to provide benefit to the patient and increases the risk of the development of drug-resistant bacteria.

6 ADVERSE REACTIONS

The following clinically significant adverse reactions are described elsewhere in the labeling:

- Myelosuppression [see Warnings and Precautions (5.1)]
- Peripheral and Optic Neuropathy [see Warnings and Precautions (5.2)]
- Serotonin Syndrome [see Warnings and Precautions (5.3)]
- Clostridioides difficile-Associated Diarrhea [see Warnings and Precautions (5.5)]
- Lactic Acidosis [see Warnings and Precautions (5.7)]
- Convulsions [see Warnings and Precautions (5.8)]
- Rhabdomyolysis [see Warnings and Precautions (5.9)]
- Hypoglycemia [see Warnings and Precautions (5.10)]
- Hyponatremia and/or Syndrome of Inappropriate Antidiuretic Hormone Secretion (SIADH) [see Warnings and Precautions (5.11)]

6.1 Clinical Trials Experience

Because clinical trials are conducted under widely varying conditions, adverse reaction rates observed in the clinical trials of a drug cannot be directly compared to rates in the clinical trials of another drug and may not reflect the rates observed in practice.

Adults

The safety of ZYVOX formulations was evaluated in 2,046 adult patients enrolled in seven Phase 3 comparator-controlled clinical trials, who were treated for up to 28 days.

Of the patients treated for uncomplicated skin and skin structure infections (uSSSIs), 25.4% of ZYVOX-treated and 19.6% of comparator-treated patients experienced at least one drug-related adverse event. For all other indications, 20.4% of ZYVOX -treated and 14.3% of comparator-treated patients experienced at least one drug-related adverse event.

Table 2 shows the incidence of all-causality, treatment-emergent adverse reactions reported in at least 1% of adult patients in these trials by dose of ZYVOX.

Table 2. Incidence (%) of Treatment–Emergent Adverse Reactions Occurring in >1% of Adult Patients Treated with ZYVOX in Comparator-Controlled Clinical Trials
ADVERSE REACTIONS | Uncomplicated Skin and Skin Structure Infections |  | All Other Indications
 | ZYVOX 400 mg by mouth every 12 hours (n=548) | Clarithromycin 250 mg by mouth every 12 hours (n=537) | ZYVOX 600 mg every 12 hours (n=1498) | All Other Comparators [Comparators included cefpodoxime proxetil 200 mg by mouth every 12 hours; ceftriaxone 1 g intravenously every 12 hours; dicloxacillin 500 mg by mouth every 6 hours; oxacillin 2 g intravenously every 6 hours; vancomycin 1 g intravenously every 12 hours.] (n=1464)
Headache | 8.8 | 8.4 | 5.7 | 4.4
Diarrhea | 8.2 | 6.1 | 8.3 | 6.4
Nausea | 5.1 | 4.5 | 6.6 | 4.6
Vomiting | 2.0 | 1.5 | 4.3 | 2.3
Dizziness | 2.6 | 3.0 | 1.8 | 1.5
Rash | 1.1 | 1.1 | 2.3 | 2.6
Anemia | 0.4 | 0 | 2.1 | 1.4
Taste alteration | 1.8 | 2.0 | 1.0 | 0.3
Vaginal moniliasis | 1.8 | 1.3 | 1.1 | 0.5
Oral moniliasis | 0.5 | 0 | 1.7 | 1.0
Abnormal liver function tests | 0.4 | 0.2 | 1.6 | 0.8
Fungal infection | 1.5 | 0.2 | 0.3 | 0.2
Tongue discoloration | 1.3 | 0 | 0.3 | 0
Localized abdominal pain | 1.3 | 0.6 | 1.2 | 0.8
Generalized abdominal pain | 0.9 | 0.4 | 1.2 | 1.0

Of the patients treated for uSSSIs, 3.5% of ZYVOX-treated and 2.4% of comparator-treated patients discontinued treatment due to drug-related adverse events. For all other indications, discontinuations due to drug-related adverse events occurred in 2.1% of ZYVOX-treated and 1.7% of comparator-treated patients. The most common reported drug-related adverse events leading to discontinuation of treatment were nausea, headache, diarrhea, and vomiting.

Pediatric Patients

The safety of ZYVOX formulations was evaluated in 215 pediatric patients ranging in age from birth through 11 years, and in 248 pediatric patients aged 5 through 17 years (146 of these 248 were age 5 through 11 and 102 were age 12 to 17). These patients were enrolled in two Phase 3 comparator-controlled clinical trials and were treated for up to 28 days. In the study of hospitalized pediatric patients (birth through 11 years) with Gram-positive infections, who were randomized 2 to 1 (linezolid: vancomycin), mortality was 6.0% (13/215) in the linezolid arm and 3.0% (3/101) in the vancomycin arm. However, given the severe underlying illness in the patient population, no causality could be established.

Of the pediatric patients treated for uSSSIs, 19.2% of ZYVOX-treated and 14.1% of comparator-treated patients experienced at least one drug-related adverse event. For all other indications, 18.8% of ZYVOX-treated and 34.3% of comparator-treated patients experienced at least one drug-related adverse event.

Table 3 shows the incidence of all-causality, treatment-emergent adverse reactions reported in more than 1% of pediatric patients (and more than 1 patient) in either treatment group in the comparator-controlled Phase 3 trials.

Table 3. Incidence (%) of Treatment-Emergent Adverse Reactions Occurring in > 1% of Pediatric Patients (and >1 Patient) in Either Treatment Group in Comparator-Controlled Clinical Trials
ADVERSE REACTIONS | Uncomplicated Skin and Skin Structure Infections [Patients 5 through 11 years of age received ZYVOX 10 mg/kg by mouth every 12 hours or cefadroxil 15 mg/kg by mouth every 12 hours. Patients 12 years or older received ZYVOX 600 mg by mouth every 12 hours or cefadroxil 500 mg by mouth every 12 hours.] |  | All Other Indications [Patients from birth through 11 years of age received ZYVOX 10 mg/kg intravenously by mouth every 8 hours or vancomycin 10 to 15 mg/kg intravenously every 6–24 hours, depending on age and renal clearance.]
 | ZYVOX (n=248) | Cefadroxil (n=251) | ZYVOX (n=215) | Vancomycin (n=101)
Diarrhea | 7.8 | 8.0 | 10.8 | 12.1
Vomiting | 2.9 | 6.4 | 9.4 | 9.1
Headache | 6.5 | 4.0 | 0.9 | 0
Anemia | 0 | 0 | 5.6 | 7.1
Thrombocytopenia | 0 | 0 | 4.7 | 2.0
Nausea | 3.7 | 3.2 | 1.9 | 0
Generalized abdominal pain | 2.4 | 2.8 | 0.9 | 2.0
Localized abdominal pain | 2.4 | 2.8 | 0.5 | 1.0
Loose stools | 1.6 | 0.8 | 2.3 | 3.0
Eosinophilia | 0.4 | 0.8 | 1.9 | 1.0
Pruritus at non-application site | 0.8 | 0.4 | 1.4 | 2.0
Vertigo | 1.2 | 0.4 | 0 | 0

Of the pediatric patients treated for uSSSIs, 1.6% of ZYVOX-treated and 2.4% of comparator-treated patients discontinued treatment due to drug-related adverse events. For all other indications, discontinuations due to drug-related adverse events occurred in 0.9% of ZYVOX-treated and 6.1% of comparator-treated patients.

Laboratory Abnormalities

ZYVOX has been associated with thrombocytopenia when used in doses up to and including 600 mg every 12 hours for up to 28 days. In Phase 3 comparator-controlled trials, the percentage of adult patients who developed a substantially low platelet count (defined as less than 75% of lower limit of normal and/or baseline) was 2.4% (range among studies: 0.3 to 10.0%) with ZYVOX and 1.5% (range among studies: 0.4 to 7.0%) with a comparator. In a study of hospitalized pediatric patients ranging in age from birth through 11 years, the percentage of patients who developed a substantially low platelet count (defined as less than 75% of lower limit of normal and/or baseline) was 12.9% with ZYVOX and 13.4% with vancomycin. In an outpatient study of pediatric patients aged from 5 through 17 years, the percentage of patients who developed a substantially low platelet count was 0% with ZYVOX and 0.4% with cefadroxil. Thrombocytopenia associated with the use of ZYVOX appears to be dependent on duration of therapy (generally greater than 2 weeks of treatment). The platelet counts for most patients returned to the normal range/baseline during the follow-up period. No related clinical adverse events were identified in Phase 3 clinical trials in patients developing thrombocytopenia. Bleeding events were identified in thrombocytopenic patients in a compassionate use program for ZYVOX; the role of linezolid in these events cannot be determined [see Warnings and Precautions (5.1)].

Changes seen in other laboratory parameters, without regard to drug relationship, revealed no substantial differences between ZYVOX and the comparators. These changes were generally not clinically significant, did not lead to discontinuation of therapy, and were reversible. The incidence of adult and pediatric patients with at least one substantially abnormal hematologic or serum chemistry value is presented in Tables 4, 5, 6, and 7.

Table 4. Percent of Adult Patients who Experienced at Least One Substantially Abnormal [<75% (<50% for neutrophils) of Lower Limit of Normal (LLN) for values normal at baseline; <75% (<50% for neutrophils) of LLN and of baseline for values abnormal at baseline.] Hematology Laboratory Value in Comparator-Controlled Clinical Trials with ZYVOX
Laboratory Assay | Uncomplicated Skin and Skin Structure Infections |  | All Other Indications
 | ZYVOX 400 mg every 12 hours | Clarithromycin 250 mg every 12 hours | ZYVOX 600 mg every 12 hours | All Other Comparators [Comparators included cefpodoxime proxetil 200 mg by mouth every 12 hours; ceftriaxone 1 g intravenously every 12 hours; dicloxacillin 500 mg by mouth every 6 hours; oxacillin 2 g intravenously every 6 hours; vancomycin 1 g intravenously every 12 hours.]
Hemoglobin (g/dL) | 0.9 | 0.0 | 7.1 | 6.6
Platelet count (× 10^3/mm^3) | 0.7 | 0.8 | 3.0 | 1.8
WBC (× 10^3/mm^3) | 0.2 | 0.6 | 2.2 | 1.3
Neutrophils (× 10^3/mm^3) | 0.0 | 0.2 | 1.1 | 1.2

Table 5. Percent of Adult Patients who Experienced at Least One Substantially Abnormal [>2 × Upper Limit of Normal (ULN) for values normal at baseline; >2 × ULN and >2 × baseline for values abnormal at baseline.] Serum Chemistry Laboratory Value in Comparator-Controlled Clinical Trials with ZYVOX
Laboratory Assay | Uncomplicated Skin and Skin Structure Infections |  | All Other Indications
 | ZYVOX 400 mg every 12 hours | Clarithromycin 250 mg every 12 hours | ZYVOX 600 mg every 12 hours | All Other Comparators [Comparators included cefpodoxime proxetil 200 mg by mouth every 12 hours; ceftriaxone 1 g intravenously every 12 hours; dicloxacillin 500 mg by mouth every 6 hours; oxacillin 2 g intravenously every 6 hours; vancomycin 1 g intravenously every 12 hours.]
AST (U/L) | 1.7 | 1.3 | 5.0 | 6.8
ALT (U/L) | 1.7 | 1.7 | 9.6 | 9.3
LDH (U/L) | 0.2 | 0.2 | 1.8 | 1.5
Alkaline phosphatase (U/L) | 0.2 | 0.2 | 3.5 | 3.1
Lipase (U/L) | 2.8 | 2.6 | 4.3 | 4.2
Amylase (U/L) | 0.2 | 0.2 | 2.4 | 2.0
Total bilirubin (mg/dL) | 0.2 | 0.0 | 0.9 | 1.1
BUN (mg/dL) | 0.2 | 0.0 | 2.1 | 1.5
Creatinine (mg/dL) | 0.2 | 0.0 | 0.2 | 0.6

Table 6. Percent of Pediatric Patients who Experienced at Least One Substantially Abnormal [<75% (<50% for neutrophils) of Lower Limit of Normal (LLN) for values normal at baseline; <75% (<50% for neutrophils) of LLN and <75% (<50% for neutrophils, <90% for hemoglobin if baseline <LLN) of baseline for values abnormal at baseline.] Hematology Laboratory Value in Comparator-Controlled Clinical Trials with ZYVOX
Laboratory Assay | Uncomplicated Skin and Skin Structure Infections [Patients 5 through 11 years of age received ZYVOX 10 mg/kg by mouth every 12 hours or cefadroxil 15 mg/kg by mouth every 12 hours. Patients 12 years or older received ZYVOX 600 mg by mouth every 12 hours or cefadroxil 500 mg by mouth every 12 hours.] |  | All Other Indications [Patients from birth through 11 years of age received ZYVOX 10 mg/kg intravenously by mouth every 8 hours or vancomycin 10 to 15 mg/kg intravenously every 6–24 hours, depending on age and renal clearance.]
 | ZYVOX | Cefadroxil | ZYVOX | Vancomycin
Hemoglobin (g/dL) | 0.0 | 0.0 | 15.7 | 12.4
Platelet count (× 10^3/mm^3) | 0.0 | 0.4 | 12.9 | 13.4
WBC (× 10^3/mm^3) | 0.8 | 0.8 | 12.4 | 10.3
Neutrophils (× 10^3/mm^3) | 1.2 | 0.8 | 5.9 | 4.3

Table 7. Percent of Pediatric Patients who Experienced at Least One Substantially Abnormal [>2 × Upper Limit of Normal (ULN) for values normal at baseline; >2 × ULN and >2 (>1.5 for total bilirubin) × baseline for values abnormal at baseline.] Serum Chemistry Laboratory Value in Comparator-Controlled Clinical Trials with ZYVOX
Laboratory Assay | Uncomplicated Skin and Skin Structure Infections [Patients 5 through 11 years of age received ZYVOX 10 mg/kg by mouth every 12 hours or cefadroxil 15 mg/kg by mouth every 12 hours. Patients 12 years or older received ZYVOX 600 mg mouth every 12 hours or cefadroxil 500 mg by mouth every 12 hours.] |  | All Other Indications [Patients from birth through 11 years of age received ZYVOX 10 mg/kg intravenously/by mouth every 8 hours or vancomycin 10 to 15 mg/kg intravenously every 6–24 hours, depending on age and renal clearance.]
 | ZYVOX | Cefadroxil | ZYVOX | Vancomycin
ALT (U/L) | 0.0 | 0.0 | 10.1 | 12.5
Lipase (U/L) | 0.4 | 1.2 | --- | ---
Amylase (U/L) | --- | --- | 0.6 | 1.3
Total bilirubin (mg/dL) | --- | --- | 6.3 | 5.2
Creatinine (mg/dL) | 0.4 | 0.0 | 2.4 | 1.0

6.2 Postmarketing Experience

The following adverse reactions have been identified during post-approval use of ZYVOX. Because these reactions are reported voluntarily from a population of uncertain size, it is not always possible to reliably estimate their frequency or establish a causal relationship to drug exposure:

- Anaphylaxis, angioedema, bullous skin disorders including severe cutaneous adverse reactions (SCAR) such as toxic epidermal necrolysis and Stevens-Johnson syndrome, and hypersensitivity vasculitis.
- Myelosuppression (including anemia, leukopenia, pancytopenia, and thrombocytopenia). Thrombocytopenia has been reported more often in patients with severe renal impairment and in patients with moderate to severe hepatic impairment [see Warnings and Precautions (5.1)]; sideroblastic anemia.
- Peripheral neuropathy, and optic neuropathy sometimes progressing to loss of vision [see Warnings and Precautions (5.2)].
- Serotonin syndrome has been reported in patients receiving concomitant serotonergic agents, including antidepressants such as selective serotonin reuptake inhibitors (SSRIs) and opioids, and ZYVOX [see Warnings and Precautions (5.3)].
- Lactic acidosis [see Warnings and Precautions (5.7)]. Although these reports have primarily been in patients treated for longer than the maximum recommended duration of 28 days, these events have also been reported in patients receiving shorter courses of therapy.
- Convulsions [see Warnings and Precautions (5.8)].
- Rhabdomyolysis [see Warnings and Precautions (5.9)].
- Hypoglycemia, including symptomatic episodes [see Warnings and Precautions (5.10)].
- Hyponatremia and/or Syndrome of Inappropriate Antidiuretic Hormone Secretion (SIADH) [see Warnings and Precautions (5.11)].
- Superficial tooth discoloration and tongue discoloration have been reported with the use of linezolid. The tooth discoloration was removable with professional dental cleaning (manual descaling) in cases with known outcome.

7 DRUG INTERACTIONS

7.1 Monoamine Oxidase Inhibitors

Linezolid is a reversible, nonselective inhibitor of monoamine oxidase [see Contraindications (4.2) and Clinical Pharmacology (12.3)].

7.2 Adrenergic and Serotonergic Agents

Linezolid has the potential for interaction with adrenergic and serotonergic agents [see Warnings and Precautions (5.3, 5.6) and Clinical Pharmacology (12.3)].

8 USE IN SPECIFIC POPULATIONS

8.1 Pregnancy

Risk Summary

Available data from published and postmarketing case reports with linezolid use in pregnant women have not identified a drug-associated risk of major birth defects, miscarriage, or adverse maternal or fetal outcomes. When administered during organogenesis, linezolid did not cause malformations in mice, rats, or rabbits at maternal exposure levels approximately 6.5 times (mice), equivalent to (rats), or 0.06 times (rabbits) the clinical therapeutic exposure, based on AUCs. However, embryo-fetal lethality was observed in mice at 6.5 times the estimated human exposure. When female rats were dosed during organogenesis through lactation, postnatal survival of pups was decreased at doses approximately equivalent to the estimated human exposure based on AUCs (see Data).

The background risk of major birth defects and miscarriage for the indicated populations is unknown. All pregnancies have a background risk of birth defect, loss, or other adverse outcomes. In the U.S. general population, the estimated background risk of major birth defects and miscarriage in clinically recognized pregnancies is 2–4% and 15–20%, respectively.

Data

Animal Data

In mice, embryo-fetal toxicities were observed only at doses that caused maternal toxicity (clinical signs and reduced body weight gain). An oral dose of 450 mg/kg/day given from Gestation Day (GD) 6–16 (6.5 times the estimated human exposure based on AUCs) correlated with increased postimplantational embryo death, including total litter loss, decreased fetal body weights, and an increased incidence of costal cartilage fusion. Neither maternal nor embryo-fetal toxicities were observed at doses up to 150 mg/kg/day. Fetal malformations were not observed.

In rats, fetal toxicity was observed at 15 and 50 mg/kg/day administered orally from GD 6–17 (exposures 0.22 times to approximately equivalent to the estimated human exposure, respectively, based on AUCs). The effects consisted of decreased fetal body weights and reduced ossification of sternebrae, a finding often seen in association with decreased fetal body weights. Fetal malformations were not observed. Maternal toxicity, in the form of reduced body weight gain, was seen at 50 mg/kg/day.

In rabbits, reduced fetal body weight occurred only in the presence of maternal toxicity (clinical signs, reduced body weight gain and food consumption) when administered at an oral dose of 15 mg/kg/day given from GD 6–20 (0.06 times the estimated human exposure based on AUCs). Fetal malformations were not observed.

When female rats were treated with 50 mg/kg/day (approximately equivalent to the estimated human exposure based on AUCs) of linezolid during pregnancy and lactation (GD 6 through Lactation Day 20), survival of pups was decreased on postnatal days 1 to 4. Male and female pups permitted to mature to reproductive age, when mated, showed an increase in preimplantation loss.

8.2 Lactation

Risk Summary

Linezolid is present in breast milk. Based on data from available published case reports, the daily dose of linezolid that the infant would receive from breastmilk would be approximately 6% to 9% of the recommended therapeutic infant dose (10 mg/kg every 8 hours). There is no information on the effects of linezolid on the breastfed infant; however, diarrhea and vomiting were the most common adverse reactions reported in clinical trials in infants receiving linezolid therapeutically [see Adverse Reactions (6.1)] and (see Clinical Considerations). There is no information on the effects of linezolid on milk production. The developmental and health benefits of breastfeeding should be considered along with the mother's clinical need for linezolid and any potential adverse effects on the breastfed child from linezolid or from the underlying maternal condition.

Clinical Considerations

Advise lactating women to monitor a breastfed infant for diarrhea and vomiting.

8.3 Females and Males of Reproductive Potential

Infertility

Males

Based on findings from studies in rats, ZYVOX may reversibly impair fertility in male patients [see Nonclinical Toxicology (13.1)].

8.4 Pediatric Use

The safety and effectiveness of ZYVOX for the treatment of pediatric patients with the following infections are supported by evidence from adequate and well-controlled studies in adults, pharmacokinetic data in pediatric patients, and additional data from a comparator-controlled study of Gram-positive infections in pediatric patients ranging in age from birth through 11 years [see Indications and Usage (1), Clinical Pharmacology (12.3) and Clinical Studies (14)]:

- nosocomial pneumonia
- complicated skin and skin structure infections
- community-acquired pneumonia (also supported by evidence from an uncontrolled study in patients ranging in age from 8 months through 12 years)
- vancomycin-resistant Enterococcus faecium infections

The safety and effectiveness of ZYVOX for the treatment of pediatric patients with the following infection have been established in a comparator-controlled study in pediatric patients ranging in age from 5 through 17 years [see Clinical Studies (14)]:

- uncomplicated skin and skin structure infections caused by Staphylococcus aureus (methicillin-susceptible strains only) or Streptococcus pyogenes

Pharmacokinetic information generated in pediatric patients with ventriculoperitoneal shunts showed variable cerebrospinal fluid (CSF) linezolid concentrations following single and multiple dosing of linezolid; therapeutic concentrations were not consistently achieved or maintained in the CSF. Therefore, the use of linezolid for the empiric treatment of pediatric patients with central nervous system infections is not recommended.

The pharmacokinetics of linezolid have been evaluated in pediatric patients from birth to 17 years of age. In general, weight-based clearance of linezolid gradually decreases with increasing age of pediatric patients. However, in preterm (gestational age < 34 weeks) neonates < 7 days of age, linezolid clearance is often lower than in full-term neonates < 7 days of age. Consequently, preterm neonates < 7 days of age may need an alternative linezolid dosing regimen of 10 mg/kg every 12 hours [see Dosage and Administration (2.1) and Clinical Pharmacology (12.3)].

In limited clinical experience, 5 out of 6 (83%) pediatric patients with infections due to Gram-positive pathogens with minimum inhibitory concentrations (MICs) of 4 mcg/mL treated with ZYVOX had clinical cures. However, pediatric patients exhibit wider variability in linezolid clearance and systemic exposure (AUC) compared with adults. In pediatric patients with a sub-optimal clinical response, particularly those with pathogens with MIC of 4 mcg/mL, lower systemic exposure, site and severity of infection, and the underlying medical condition should be considered when assessing clinical response [see Clinical Pharmacology (12.3) and Dosage and Administration (2)].

8.5 Geriatric Use

Of the 2,046 patients treated with ZYVOX in Phase 3 comparator-controlled clinical trials, 589 (29%) were 65 years or older and 253 (12%) were 75 years or older. No overall differences in safety or effectiveness were observed between these patients and younger patients, and other reported clinical experience has not identified differences in responses between the elderly and younger patients, but greater sensitivity of some older individuals cannot be ruled out.

10 OVERDOSAGE

In the event of overdosage, supportive care is advised, with maintenance of glomerular filtration. Hemodialysis may facilitate more rapid elimination of linezolid. In a Phase 1 clinical trial, approximately 30% of a dose of linezolid was removed during a 3-hour hemodialysis session beginning 3 hours after the dose of linezolid was administered. Data are not available for removal of linezolid with peritoneal dialysis or hemoperfusion. Clinical signs of acute toxicity in animals were decreased activity and ataxia in rats and vomiting and tremors in dogs treated with 3,000 mg/kg/day and 2,000 mg/kg/day, respectively.

11 DESCRIPTION

ZYVOX I.V. Injection, ZYVOX Tablets, and ZYVOX for Oral Suspension contain linezolid, which is a synthetic antibacterial agent of the oxazolidinone class. The chemical name for linezolid is (S)-N-[[3-[3-Fluoro-4-(4-morpholinyl)phenyl]-2-oxo-5-oxazolidinyl] methyl]-acetamide.

The empirical formula is C16H20FN3O4. Its molecular weight is 337.35, and its chemical structure is represented below:

ZYVOX I.V. Injection is supplied as a ready-to-use sterile isotonic solution for intravenous infusion. Each mL contains 2 mg of linezolid. Inactive ingredients are dextrose monohydrate 50.24 mg/mL in an aqueous vehicle for intravenous administration, sodium citrate dihydrate 1.64 mg/mL, and citric acid anhydrous 0.85 mg/mL. Sodium hydroxide NF and/or hydrochloric acid NF are used to adjust the pH. The sodium (Na^+) content is 0.38 mg/mL (5 mEq/300 mL bag and 1.7 mEq/100 mL bag).

ZYVOX Tablet for oral administration contains 600 mg linezolid as a film-coated compressed tablet. Inactive ingredients are carnauba wax, corn starch, hydroxypropylcellulose, hypromellose, magnesium stearate, microcrystalline cellulose, polyethylene glycol, sodium starch glycolate, and titanium dioxide. The sodium (Na^+) content is 2.92 mg per 600 mg tablet (0.1 mEq/tablet).

ZYVOX for Oral Suspension is supplied as an orange-flavored granule/powder for constitution into a suspension for oral administration. Following constitution, each 5 mL contains 100 mg of linezolid. Inactive ingredients are aspartame, citric acid, colloidal silicon dioxide, flavors, mannitol, microcrystalline cellulose and carboxymethylcellulose sodium, sodium benzoate, sodium chloride, sodium citrate, sucrose, and xanthan gum [see Patient Counseling Information (17)]. The sodium (Na^+) content is 8.52 mg/5 mL (0.4 mEq/5 mL).

12 CLINICAL PHARMACOLOGY

12.1 Mechanism of Action

ZYVOX is an antibacterial drug [see Microbiology (12.4)].

12.2 Pharmacodynamics

In a randomized, positive- and placebo-controlled crossover thorough QT study, 40 healthy subjects were administered a single ZYVOX 600 mg dose via a 1 hour IV infusion, a single ZYVOX 1,200 mg dose via a 1 hour IV infusion, placebo, and a single oral dose of positive control. At both the 600 mg and 1,200 mg ZYVOX doses, no significant effect on QTc interval was detected at peak plasma concentration or at any other time.

12.3 Pharmacokinetics

The mean pharmacokinetic parameters of linezolid in adults after single and multiple oral and intravenous doses are summarized in Table 8. Plasma concentrations of linezolid at steady-state after oral doses of 600 mg given every 12 hours are shown in Figure 1.

Table 8. Mean (Standard Deviation) Pharmacokinetic Parameters of Linezolid in Adults
Dose of Linezolid | Cmax mcg/mL | Cmin mcg/mL | Tmax hrs | AUC [AUC for single dose = AUC0–∞; for multiple dose = AUC0–τ] mcg∙h/mL | t1/2 hrs | CL mL/min
400 mg tablet
single dose [Data dose-normalized from 375 mg] | 8.10 (1.83) | --- | 1.52 (1.01) | 55.10 (25.00) | 5.20 (1.50) | 146 (67)
every 12; hours | 11.00 (4.37) | 3.08 (2.25) | 1.12 (0.47) | 73.40 (33.50) | 4.69 (1.70) | 110 (49)
600 mg tablet
single dose | 12.70 (3.96) | --- | 1.28 (0.66) | 91.40 (39.30) | 4.26 (1.65) | 127 (48)
every 12; hours | 21.20 (5.78) | 6.15 (2.94) | 1.03 (0.62) | 138.00 (42.10) | 5.40 (2.06) | 80 (29)
600 mg IV injection [Data dose-normalized from 625 mg, intravenous dose was given as 0.5-hour infusion.]
single dose | 12.90 (1.60) | --- | 0.50 (0.10) | 80.20 (33.30) | 4.40 (2.40) | 138 (39)
every 12; hours | 15.10 (2.52) | 3.68 (2.36) | 0.51 (0.03) | 89.70 (31.00) | 4.80 (1.70) | 123 (40)
600 mg oral suspension
single dose | 11.00 (2.76) | --- | 0.97 (0.88) | 80.80 (35.10) | 4.60 (1.71) | 141 (45)
Cmax = Maximum plasma concentration; Cmin = Minimum plasma concentration; Tmax = Time to Cmax; AUC = Area under concentration-time curve; t1/2 = Elimination half-life; CL = Systemic clearance

Figure 1. Plasma Concentrations of Linezolid in Adults at Steady-State Following Oral Dosing Every 12 Hours (Mean ± Standard Deviation, n=16)

Absorption

Linezolid is extensively absorbed after oral dosing. Maximum plasma concentrations are reached approximately 1 to 2 hours after dosing, and the absolute bioavailability is approximately 100%. Therefore, linezolid may be given orally or intravenously without dose adjustment.

Linezolid may be administered without regard to the timing of meals. The time to reach the maximum concentration is delayed from 1.5 hours to 2.2 hours and Cmax is decreased by about 17% when high fat food is given with linezolid. However, the total exposure measured as AUC0–∞ is similar under both conditions.

Distribution

Animal and human pharmacokinetic studies have demonstrated that linezolid readily distributes to well-perfused tissues. The plasma protein binding of linezolid is approximately 31% and is concentration-independent. The volume of distribution of linezolid at steady-state averaged 40 to 50 liters in healthy adult volunteers.

Linezolid concentrations have been determined in various fluids from a limited number of subjects in Phase 1 volunteer studies following multiple dosing of linezolid. The ratio of linezolid in saliva relative to plasma was 1.2 to 1 and the ratio of linezolid in sweat relative to plasma was 0.55 to 1.

Metabolism

Linezolid is primarily metabolized by oxidation of the morpholine ring, which results in two inactive ring-opened carboxylic acid metabolites: the aminoethoxyacetic acid metabolite (A), and the hydroxyethyl glycine metabolite (B). Formation of metabolite A is presumed to be formed via an enzymatic pathway whereas metabolite B is mediated by a non-enzymatic chemical oxidation mechanism in vitro. In vitro studies have demonstrated that linezolid is minimally metabolized and may be mediated by human cytochrome P450. However, the metabolic pathway of linezolid is not fully understood.

Excretion

Nonrenal clearance accounts for approximately 65% of the total clearance of linezolid. Under steady-state conditions, approximately 30% of the dose appears in the urine as linezolid, 40% as metabolite B, and 10% as metabolite A. The mean renal clearance of linezolid is 40 mL/min which suggests net tubular reabsorption. Virtually no linezolid appears in the feces, while approximately 6% of the dose appears in the feces as metabolite B, and 3% as metabolite A.

A small degree of nonlinearity in clearance was observed with increasing doses of linezolid, which appears to be due to lower renal and nonrenal clearance of linezolid at higher concentrations. However, the difference in clearance was small and was not reflected in the apparent elimination half-life.

Specific Populations

Geriatric Patients

The pharmacokinetics of linezolid are not significantly altered in elderly patients (65 years or older). Therefore, dose adjustment for geriatric patients is not necessary.

Pediatric Patients

The pharmacokinetics of linezolid following a single intravenous dose were investigated in pediatric patients ranging in age from birth through 17 years (including premature and full-term neonates), in healthy adolescent subjects ranging in age from 12 through 17 years, and in pediatric patients ranging in age from 1 week through 12 years. The pharmacokinetic parameters of linezolid are summarized in Table 9 for the pediatric populations studied and healthy adult subjects after administration of single intravenous doses.

The Cmax and the volume of distribution (Vss) of linezolid are similar regardless of age in pediatric patients. However, plasma clearance of linezolid varies as a function of age. With the exclusion of pre-term neonates less than one week of age, weight-based clearance is most rapid in the youngest age groups ranging from < 1 week old to 11 years, resulting in lower single-dose systemic exposure (AUC) and a shorter half-life as compared with adults. As the age of pediatric patients increases, the weight-based clearance of linezolid gradually decreases, and by adolescence mean clearance values approach those observed for the adult population. There is increased inter-subject variability in linezolid clearance and systemic drug exposure (AUC) across all pediatric age groups as compared with adults.

Similar mean daily AUC values were observed in pediatric patients from birth to 11 years of age dosed every 8 hours relative to adolescents or adults dosed every 12 hours. Therefore, the dosage for pediatric patients up to 11 years of age should be 10 mg/kg every 8 hours. Pediatric patients 12 years and older should receive 600 mg every 12 hours [see Dosage and Administration (2)].

Table 9. Pharmacokinetic Parameters of Linezolid in Pediatrics and Adults Following a Single Intravenous Infusion of 10 mg/kg or 600 mg Linezolid (Mean: (%CV); [Min, Max Values])
Age Group | Cmax mcg/mL | Vss L/kg | AUC [AUC = Single dose AUC0–∞] mcg∙h/mL | t 1/2 hrs | CL mL/min/kg
Neonatal Patients
Pre-term [In this data set, "pre-term" is defined as <34 weeks gestational age (Note: Only 1 patient enrolled was pre-term with a postnatal age between 1 week and 28 days)] | 12.7 (30%) | 0.81 (24%) | 108 (47%) | 5.6 (46%) | 2.0 (52%)
< 1 week (N=9) [Dose of 10 mg/kg] | [9.6, 22.2] | [0.43, 1.05] | [41, 191] | [2.4, 9.8] | [0.9, 4.0]
Full-term [In this data set, "full-term" is defined as ≥34 weeks gestational age] | 11.5 (24%) | 0.78 (20%) | 55 (47%) | 3.0 (55%) | 3.8 (55%)
< 1 week (N=10) | [8.0, 18.3] | [0.45, 0.96] | [19, 103] | [1.3, 6.1] | [1.5, 8.8]
Full-term | 12.9 (28%) | 0.66 (29%) | 34 (21%) | 1.5 (17%) | 5.1 (22%)
≥ 1 week to ≤ 28 days (N=10) | [7.7, 21.6] | [0.35, 1.06] | [23, 50] | [1.2, 1.9] | [3.3, 7.2]
Infant Patients
> 28 days to < 3 Months (N=12) | 11.0 (27%) [7.2, 18.0] | 0.79 (26%) [0.42, 1.08] | 33 (26%) [17, 48] | 1.8 (28%) [1.2, 2.8] | 5.4 (32%) [3.5, 9.9]
Pediatric Patients
3 months through 11 years (N=59) | 15.1 (30%) [6.8, 36.7] | 0.69 (28%) [0.31, 1.50] | 58 (54%) [19, 153] | 2.9 (53%) [0.9, 8.0] | 3.8 (53%) [1.0, 8.5]
Adolescent Subjects and Patients
12 through 17 years [Dose of 600 mg or 10 mg/kg up to a maximum of 600 mg] (N=36) | 16.7 (24%) [9.9, 28.9] | 0.61 (15%) [0.44, 0.79] | 95 (44%) [32, 178] | 4.1 (46%) [1.3, 8.1] | 2.1 (53%) [0.9, 5.2]
Adult Subjects [Dose normalized to 600 mg] | 12.5 (21%) | 0.65 (16%) | 91 (33%) | 4.9 (35%) | 1.7 (34%)
(N= 29) | [8.2, 19.3] | [0.45, 0.84] | [53, 155] | [1.8, 8.3] | [0.9, 3.3]
Cmax = Maximum plasma concentration; Vss= Volume of distribution; AUC = Area under concentration-time curve;
t1/2 = Apparent elimination half-life; CL = Systemic clearance normalized for body weight

Gender

Females have a slightly lower volume of distribution of linezolid than males. Plasma concentrations are higher in females than in males, which is partly due to body weight differences. After a 600-mg dose, mean oral clearance is approximately 38% lower in females than in males. However, there are no significant gender differences in mean apparent elimination-rate constant or half-life. Thus, drug exposure in females is not expected to substantially increase beyond levels known to be well tolerated. Therefore, dose adjustment by gender does not appear to be necessary.

Renal Impairment

The pharmacokinetics of the parent drug, linezolid, are not altered in patients with any degree of renal impairment; however, the two primary metabolites of linezolid accumulate in patients with renal impairment, with the amount of accumulation increasing with the severity of renal dysfunction (see Table 10). The pharmacokinetics of linezolid and its two metabolites have also been studied in patients with end-stage renal disease (ESRD) receiving hemodialysis. In the ESRD study, 14 patients were dosed with linezolid 600 mg every 12 hours for 14.5 days (see Table 11). Because similar plasma concentrations of linezolid are achieved regardless of renal function, no dose adjustment is recommended for patients with renal impairment. However, given the absence of information on the clinical significance of accumulation of the primary metabolites, use of linezolid in patients with renal impairment should be weighed against the potential risks of accumulation of these metabolites. Both linezolid and the two metabolites are eliminated by hemodialysis. No information is available on the effect of peritoneal dialysis on the pharmacokinetics of linezolid. Approximately 30% of a dose was eliminated in a 3-hour hemodialysis session beginning 3 hours after the dose of linezolid was administered; therefore, linezolid should be given after hemodialysis.

Table 10. Mean (Standard Deviation) AUCs and Elimination Half-lives of Linezolid and Metabolites A and B in Patients with Varying Degrees of Renal Impairment After a Single 600 mg Oral Dose of Linezolid
Parameter | Healthy Subjects CLCR > 80 mL/min | Moderate Renal Impairment 30 < CLCR < 80 mL/min | Severe Renal Impairment 10 < CLCR < 30 mL/min
LINEZOLID
AUC0–∞, mcg h/mL | 110 (22) | 128 (53) | 127 (66)
t1/2, hours | 6.4 (2.2) | 6.1 (1.7) | 7.1 (3.7)
METABOLITE A
AUC0–48, mcg h/mL | 7.6 (1.9) | 11.7 (4.3) | 56.5 (30.6)
t1/2, hours | 6.3 (2.1) | 6.6 (2.3) | 9.0 (4.6)
METABOLITE B [Metabolite B is the major metabolite of linezolid.]
AUC0–48, mcg h/mL | 30.5 (6.2) | 51.1 (38.5) | 203 (92)
t1/2, hours | 6.6 (2.7) | 9.9 (7.4) | 11.0 (3.9)

Table 11. Mean (Standard Deviation) AUCs and Elimination Half-lives of Linezolid and Metabolites A and B in Subjects with End-Stage Renal Disease (ESRD) After the Administration of 600 mg Linezolid Every 12 Hours for 14.5 Days
Parameter | ESRD Subjects [between hemodialysis sessions]
LINEZOLID
AUC0–12, mcg h/mL (after last dose) | 181 (52.3)
t1/2, h (after last dose) | 8.3 (2.4)
METABOLITE A
AUC0–12, mcg h/mL (after last dose) | 153 (40.6)
t1/2, h (after last dose) | 15.9 (8.5)
METABOLITE B [Metabolite B is the major metabolite of linezolid.]
AUC0–12, mcg h/mL (after last dose) | 356 (99.7)
t1/2, h (after last dose) | 34.8 (23.1)

Hepatic Impairment

The pharmacokinetics of linezolid are not altered in patients (n=7) with mild-to-moderate hepatic impairment (Child-Pugh class A or B). On the basis of the available information, no dose adjustment is recommended for patients with mild-to-moderate hepatic impairment. The pharmacokinetics of linezolid in patients with severe hepatic impairment have not been evaluated.

Drug Interactions

Drugs Metabolized by Cytochrome P450

Linezolid is not an inducer of cytochrome P450 (CYP450) in rats. In addition, linezolid does not inhibit the activities of clinically significant human CYP isoforms (e.g., 1A2, 2C9, 2C19, 2D6, 2E1, 3A4). Therefore, linezolid is not expected to affect the pharmacokinetics of other drugs metabolized by these major enzymes. Concurrent administration of linezolid does not substantially alter the pharmacokinetic characteristics of (S)-warfarin, which is extensively metabolized by CYP2C9. Drugs such as warfarin and phenytoin, which are CYP2C9 substrates, may be given with linezolid without changes in dosage regimen.

Antibacterial Drugs

Aztreonam: The pharmacokinetics of linezolid or aztreonam are not altered when administered together.

Gentamicin: The pharmacokinetics of linezolid or gentamicin are not altered when administered together.

Antioxidants

The potential for drug-drug interactions with linezolid and the antioxidants Vitamin C and Vitamin E was studied in healthy volunteers. Subjects were administered a 600 mg oral dose of linezolid on Day 1, and another 600 mg dose of linezolid on Day 8. On Days 2–9, subjects were given either Vitamin C (1,000 mg/day) or Vitamin E (800 IU/ day). The AUC0–∞ of linezolid increased 2.3% when co-administered with Vitamin C and 10.9% when co-administered with Vitamin E. No linezolid dose adjustment is recommended during co-administration with Vitamin C or Vitamin E.

Strong CYP 3A4 Inducers

Rifampin: The effect of rifampin on the pharmacokinetics of linezolid was evaluated in a study of 16 healthy adult males. Volunteers were administered oral linezolid 600 mg twice daily for 5 doses with and without rifampin 600 mg once daily for 8 days. Co-administration of rifampin with linezolid resulted in a 21% decrease in linezolid Cmax [90% CI, 15% – 27%] and a 32% decrease in linezolid AUC0–12 [90% CI, 27% – 37%]. The clinical significance of this interaction is unknown. The mechanism of this interaction is not fully understood and may be related to the induction of hepatic enzymes. Other strong inducers of hepatic enzymes (e.g. carbamazepine, phenytoin, phenobarbital) could cause a similar or smaller decrease in linezolid exposure.

Monoamine Oxidase Inhibition

Linezolid is a reversible, nonselective inhibitor of monoamine oxidase. Therefore, linezolid has the potential for interaction with adrenergic and serotonergic agents.

Adrenergic Agents

Some individuals receiving ZYVOX may experience a reversible enhancement of the pressor response to indirect-acting sympathomimetic agents, vasopressor or dopaminergic agents. Commonly used drugs such as phenylpropanolamine and pseudoephedrine have been specifically studied. Initial doses of adrenergic agents, such as dopamine or epinephrine, should be reduced and titrated to achieve the desired response.

Tyramine: A significant pressor response has been observed in normal adult subjects receiving linezolid and tyramine doses of more than 100 mg. Therefore, patients receiving linezolid need to avoid consuming large amounts of foods or beverages with high tyramine content [see Patient Counseling Information (17)].

Pseudoephedrine HCl or phenylpropanolamine HCl: A reversible enhancement of the pressor response of either pseudoephedrine HCl (PSE) or phenylpropanolamine HCl (PPA) is observed when linezolid is administered to healthy normotensive subjects [see Warnings and Precautions (5.6) and Drug Interactions (7)]. A similar study has not been conducted in hypertensive patients. The interaction studies conducted in normotensive subjects evaluated the blood pressure and heart rate effects of placebo, PPA or PSE alone, linezolid alone, and the combination of steady-state linezolid (600 mg every 12 hours for 3 days) with two doses of PPA (25 mg) or PSE (60 mg) given 4 hours apart. Heart rate was not affected by any of the treatments. Blood pressure was increased with both combination treatments. Maximum blood pressure levels were seen 2 to 3 hours after the second dose of PPA or PSE, and returned to baseline 2 to 3 hours after peak. The results of the PPA study follow, showing the mean (and range) maximum systolic blood pressure in mm Hg: placebo = 121 (103 to 158); linezolid alone = 120 (107 to 135); PPA alone = 125 (106 to 139); PPA with linezolid = 147 (129 to 176). The results from the PSE study were similar to those in the PPA study. The mean maximum increase in systolic blood pressure over baseline was 32 mm Hg (range: 20–52 mm Hg) and 38 mm Hg (range: 18–79 mm Hg) during co-administration of linezolid with pseudoephedrine or phenylpropanolamine, respectively.

Serotonergic Agents

Dextromethorphan: The potential drug-drug interaction with dextromethorphan was studied in healthy volunteers. Subjects were administered dextromethorphan (two 20-mg doses given 4 hours apart) with or without linezolid. No serotonin syndrome effects (confusion, delirium, restlessness, tremors, blushing, diaphoresis, hyperpyrexia) have been observed in normal subjects receiving linezolid and dextromethorphan.

12.4 Microbiology

Mechanism of Action

Linezolid is a synthetic antibacterial agent of the oxazolidinone class, which has clinical utility in the treatment of infections caused by aerobic Gram-positive bacteria. The in vitro spectrum of activity of linezolid also includes certain Gram-negative bacteria and anaerobic bacteria. Linezolid binds to a site on the bacterial 23S ribosomal RNA of the 50S subunit and prevents the formation of a functional 70S initiation complex, which is essential for bacterial reproduction. The results of time-kill studies have shown linezolid to be bacteriostatic against enterococci and staphylococci. For streptococci, linezolid was found to be bactericidal for the majority of isolates.

Resistance

In vitro studies have shown that point mutations in the 23S rRNA are associated with linezolid resistance. Reports of vancomycin-resistant Enterococcus faecium becoming resistant to linezolid during its clinical use have been published. There are reports of Staphylococcus aureus (methicillin-resistant) developing resistance to linezolid during clinical use. The linezolid resistance in these organisms is associated with a point mutation in the 23S rRNA (substitution of thymine for guanine at position 2576) of the organism. Organisms resistant to oxazolidinones via mutations in chromosomal genes encoding 23S rRNA or ribosomal proteins (L3 and L4) are generally cross-resistant to linezolid. Also linezolid resistance in staphylococci mediated by the enzyme methyltransferase has been reported. This resistance is mediated by the cfr (chloramphenicol-florfenicol) gene located on a plasmid which is transferable between staphylococci.

Interaction with Other Antimicrobial Drugs

In vitro studies have demonstrated additivity or indifference between linezolid and vancomycin, gentamicin, rifampin, imipenem-cilastatin, aztreonam, ampicillin, or streptomycin.

Linezolid has been shown to be active against most isolates of the following microorganisms, both in vitro and in clinical infections [see Indications and Usage (1)].

Gram-positive bacteria

Enterococcus faecium (vancomycin-resistant isolates only)

Staphylococcus aureus (including methicillin-resistant isolates)

Streptococcus agalactiae

Streptococcus pneumoniae

Streptococcus pyogenes

The following in vitro data are available, but their clinical significance is unknown. Greater than 90% of the following bacteria exhibit an in vitro MIC less than or equal to the linezolid-susceptible breakpoint for organisms of similar genus. The safety and effectiveness of linezolid in treating clinical infections due to these bacteria have not been established in adequate and well-controlled clinical trials.

Gram-positive bacteria

Enterococcus faecalis (including vancomycin-resistant isolates)

Enterococcus faecium (vancomycin-susceptible isolates)

Staphylococcus epidermidis (including methicillin-resistant isolates)

Staphylococcus haemolyticus

Viridans group streptococci

Gram-negative bacteria

Pasteurella multocida

Susceptibility Testing

For specific information regarding susceptibility test interpretive criteria and associated test methods and quality control standards recognized by FDA for this drug, please see: https://www.fda.gov/STIC.

13 NONCLINICAL TOXICOLOGY

13.1 Carcinogenesis, Mutagenesis, Impairment of Fertility

Lifetime studies in animals have not been conducted to evaluate the carcinogenic potential of linezolid. Neither mutagenic nor clastogenic potential was found in a battery of tests including: assays for mutagenicity (Ames bacterial reversion and CHO cell mutation), an in vitro unscheduled DNA synthesis (UDS) assay, an in vitro chromosome aberration assay in human lymphocytes, and an in vivo mouse micronucleus assay.

Linezolid did not affect the fertility or reproductive performance of adult female rats given oral doses of up to 100 mg/kg/day for 14 days prior to mating through Gestation Day 7. It reversibly decreased fertility and reproductive performance in adult male rats when given at doses ≥ 50 mg/kg/day, with exposures approximately equal to or greater than the expected human exposure level (exposure comparisons are based on AUCs). The reversible fertility effects were mediated through altered spermatogenesis. Affected spermatids contained abnormally formed and oriented mitochondria and were non-viable. Epithelial cell hypertrophy and hyperplasia in the epididymis was observed in conjunction with decreased fertility. Similar epididymal changes were not seen in dogs.

In sexually mature male rats exposed to drug as juveniles, mildly decreased fertility was observed following treatment with linezolid through most of their period of sexual development (50 mg/kg/day from days 7 to 36 of age, and 100 mg/kg/day from days 37 to 55 of age), with exposures up to 1.7 times greater than mean AUCs observed in pediatric patients aged 3 months to 11 years. Decreased fertility was not observed with shorter treatment periods, corresponding to exposure in utero through the early neonatal period (gestation day 6 through postnatal day 5), neonatal exposure (postnatal days 5 to 21), or to juvenile exposure (postnatal days 22 to 35). Reversible reductions in sperm motility and altered sperm morphology were observed in rats treated from postnatal day 22 to 35.

13.2 Animal Toxicology and/or Pharmacology

Target organs of linezolid toxicity were similar in juvenile and adult rats and dogs. Dose- and time-dependent myelosuppression, as evidenced by bone marrow hypocellularity/decreased hematopoiesis, decreased extramedullary hematopoiesis in spleen and liver, and decreased levels of circulating erythrocytes, leukocytes, and platelets have been seen in animal studies. Lymphoid depletion occurred in thymus, lymph nodes, and spleen. Generally, the lymphoid findings were associated with anorexia, weight loss, and suppression of body weight gain, which may have contributed to the observed effects.

In rats administered linezolid orally for 6 months, non-reversible, minimal to mild axonal degeneration of sciatic nerves was observed at 80 mg/kg/day; minimal degeneration of the sciatic nerve was also observed in 1 male at this dose level at a 3-month interim necropsy. Sensitive morphologic evaluation of perfusion-fixed tissues was conducted to investigate evidence of optic nerve degeneration. Minimal to moderate optic nerve degeneration was evident in 2 male rats after 6 months of dosing, but the direct relationship to drug was equivocal because of the acute nature of the finding and its asymmetrical distribution. The nerve degeneration observed was microscopically comparable to spontaneous unilateral optic nerve degeneration reported in aging rats and may be an exacerbation of common background change.

These effects were observed at exposure levels that are comparable to those observed in some human subjects. The hematopoietic and lymphoid effects were reversible, although in some studies, reversal was incomplete within the duration of the recovery period.

14 CLINICAL STUDIES

14.1 Adults

Nosocomial Pneumonia

Adult patients with clinically and radiologically documented nosocomial pneumonia were enrolled in a randomized, multi-center, double-blind trial. Patients were treated for 7 to 21 days. One group received ZYVOX I.V. Injection 600 mg every 12 hours, and the other group received vancomycin 1 g every 12 hours intravenously. Both groups received concomitant aztreonam (1 to 2 g every 8 hours intravenously), which could be continued if clinically indicated. There were 203 linezolid-treated and 193 vancomycin-treated patients enrolled in the study. One hundred twenty-two (60%) linezolid-treated patients and 103 (53%) vancomycin-treated patients were clinically evaluable. The cure rates in clinically evaluable patients were 57% for linezolid-treated patients and 60% for vancomycin-treated patients. The cure rates in clinically evaluable patients with ventilator-associated pneumonia were 47% for linezolid-treated patients and 40% for vancomycin-treated patients. A modified intent-to-treat (MITT) analysis of 94 linezolid-treated patients and 83 vancomycin-treated patients included subjects who had a pathogen isolated before treatment. The cure rates in the MITT analysis were 57% in linezolid-treated patients and 46% in vancomycin-treated patients. The cure rates by pathogen for microbiologically evaluable patients are presented in Table 12.

Table 12. Cure Rates at the Test-of-Cure Visit for Microbiologically Evaluable Adult Patients with Nosocomial Pneumonia
 | Cured
Pathogen | ZYVOX n/N (%) | Vancomycin n/N (%)
Staphylococcus aureus | 23/38 (61) | 14/23 (61)
Methicillin-resistant S. aureus | 13/22 (59) | 7/10 (70)
Streptococcus pneumoniae | 9/9 (100) | 9/10 (90)

Complicated Skin and Skin Structure Infections

Adult patients with clinically documented complicated skin and skin structure infections were enrolled in a randomized, multi-center, double-blind, double-dummy trial comparing study medications administered intravenously followed by medications given orally for a total of 10 to 21 days of treatment. One group of patients received ZYVOX I.V. Injection 600 mg every 12 hours followed by ZYVOX Tablets 600 mg every 12 hours; the other group received oxacillin 2 g every 6 hours intravenously followed by dicloxacillin 500 mg every 6 hours orally. Patients could receive concomitant aztreonam if clinically indicated. There were 400 linezolid-treated and 419 oxacillin-treated patients enrolled in the study. Two hundred forty-five (61%) linezolid-treated patients and 242 (58%) oxacillin-treated patients were clinically evaluable. The cure rates in clinically evaluable patients were 90% in linezolid-treated patients and 85% in oxacillin-treated patients. A modified intent-to-treat (MITT) analysis of 316 linezolid-treated patients and 313 oxacillin-treated patients included subjects who met all criteria for study entry. The cure rates in the MITT analysis were 86% in linezolid-treated patients and 82% in oxacillin-treated patients. The cure rates by pathogen for microbiologically evaluable patients are presented in Table 13.

Table 13. Cure Rates at the Test-of-Cure Visit for Microbiologically Evaluable Adult Patients with Complicated Skin and Skin Structure Infections
 | Cured
Pathogen | ZYVOX n/N (%) | Oxacillin/Dicloxacillin n/N (%)
Staphylococcus aureus | 73/83 (88) | 72/84 (86)
Methicillin-resistant S. aureus | 2/3 (67) | 0/0 (-)
Streptococcus agalactiae | 6/6 (100) | 3/6 (50)
Streptococcus pyogenes | 18/26 (69) | 21/28 (75)

A separate study provided additional experience with the use of ZYVOX in the treatment of methicillin-resistant Staphylococcus aureus (MRSA) infections. This was a randomized, open-label trial in hospitalized adult patients with documented or suspected MRSA infection.

One group of patients received ZYVOX I.V. Injection 600 mg every 12 hours followed by ZYVOX Tablets 600 mg every 12 hours. The other group of patients received vancomycin 1 g every 12 hours intravenously. Both groups were treated for 7 to 28 days, and could receive concomitant aztreonam or gentamicin if clinically indicated. The cure rates in microbiologically evaluable patients with MRSA skin and skin structure infection were 26/33 (79%) for linezolid-treated patients and 24/33 (73%) for vancomycin-treated patients.

Diabetic Foot Infections

Adult diabetic patients with clinically documented complicated skin and skin structure infections ("diabetic foot infections") were enrolled in a randomized (2:1 ratio), multi-center, open-label trial comparing study medications administered intravenously or orally for a total of 14 to 28 days of treatment. One group of patients received ZYVOX 600 mg every 12 hours intravenously or orally; the other group received ampicillin/sulbactam 1.5 to 3 g intravenously or amoxicillin/clavulanate 500 to 875 mg every 8 to 12 hours orally. In countries where ampicillin/sulbactam is not marketed, amoxicillin/clavulanate 500 mg to 2 g every 6 hours was used for the intravenous regimen. Patients in the comparator group could also be treated with vancomycin 1 g every 12 hours intravenously if MRSA was isolated from the foot infection. Patients in either treatment group who had Gram-negative bacilli isolated from the infection site could also receive aztreonam 1 to 2 g every 8–12 hours intravenously. All patients were eligible to receive appropriate adjunctive treatment methods, such as debridement and off-loading, as typically required in the treatment of diabetic foot infections, and most patients received these treatments. There were 241 linezolid-treated and 120 comparator-treated patients in the intent-to-treat (ITT) study population. Two hundred twelve (86%) linezolid-treated patients and 105 (85%) comparator-treated patients were clinically evaluable. In the ITT population, the cure rates were 68.5% (165/241) in linezolid-treated patients and 64% (77/120) in comparator-treated patients, where those with indeterminate and missing outcomes were considered failures. The cure rates in the clinically evaluable patients (excluding those with indeterminate and missing outcomes) were 83% (159/192) and 73% (74/101) in the linezolid- and comparator-treated patients, respectively. A critical post-hoc analysis focused on 121 linezolid-treated and 60 comparator-treated patients who had a Gram-positive pathogen isolated from the site of infection or from blood, who had less evidence of underlying osteomyelitis than the overall study population, and who did not receive prohibited antimicrobials. Based upon that analysis, the cure rates were 71% (86/121) in the linezolid-treated patients and 63% (38/60) in the comparator-treated patients. None of the above analyses were adjusted for the use of adjunctive therapies. The cure rates by pathogen for microbiologically evaluable patients are presented in Table 14.

Table 14. Cure Rates at the Test-of-Cure Visit for Microbiologically Evaluable Adult Patients with Diabetic Foot Infections
 | Cured
Pathogen | ZYVOX n/N (%) | Comparator n/N (%)
Staphylococcus aureus | 49/63 (78) | 20/29 (69)
Methicillin-resistant S. aureus | 12/17 (71) | 2/3 (67)
Streptococcus agalactiae | 25/29 (86) | 9/16 (56)

Vancomycin-Resistant Enterococcal Infections

Adult patients with documented or suspected vancomycin-resistant enterococcal infection were enrolled in a randomized, multi-center, double-blind trial comparing a high dose of ZYVOX (600 mg) with a low dose of ZYVOX (200 mg) given every 12 hours either intravenously (IV) or orally for 7 to 28 days. Patients could receive concomitant aztreonam or aminoglycosides. There were 79 patients randomized to high-dose linezolid and 66 to low-dose linezolid. The intent-to-treat (ITT) population with documented vancomycin-resistant enterococcal infection at baseline consisted of 65 patients in the high-dose arm and 52 in the low-dose arm.

The cure rates for the ITT population with documented vancomycin-resistant enterococcal infection at baseline are presented in Table 15 by source of infection. These cure rates do not include patients with missing or indeterminate outcomes. The cure rate was higher in the high-dose arm than in the low-dose arm, although the difference was not statistically significant at the 0.05 level.

Table 15. Cure Rates at the Test-of-Cure Visit for ITT Adult Patients with Documented Vancomycin-Resistant Enterococcal Infections at Baseline
Source of Infection | Cured
Source of Infection | ZYVOX 600 mg every 12 hours n/N (%) | ZYVOX 200 mg every 12 hours n/N (%)
Any site | 39/58 (67) | 24/46 (52)
Any site with associated bacteremia | 10/17 (59) | 4/14 (29)
Bacteremia of unknown origin | 5/10 (50) | 2/7 (29)
Skin and skin structure | 9/13 (69) | 5/5 (100)
Urinary tract | 12/19 (63) | 12/20 (60)
Pneumonia | 2/3 (67) | 0/1 (0)
Other [Includes sources of infection such as hepatic abscess, biliary sepsis, necrotic gall bladder, pericolonic abscess, pancreatitis, and catheter-related infection.] | 11/13 (85) | 5/13 (39)

14.2 Pediatric Patients

Infections due to Gram-positive Bacteria

A safety and efficacy study provided experience on the use of ZYVOX in pediatric patients for the treatment of nosocomial pneumonia, complicated skin and skin structure infections, and other infections due to Gram-positive bacterial pathogens, including methicillin-resistant and -susceptible Staphylococcus aureus and vancomycin-resistant Enterococcus faecium. Pediatric patients ranging in age from birth through 11 years with infections caused by the documented or suspected Gram-positive bacteria were enrolled in a randomized, open-label, comparator-controlled trial. One group of patients received ZYVOX I.V. Injection 10 mg/kg every 8 hours followed by ZYVOX for Oral Suspension 10 mg/kg every 8 hours. A second group received vancomycin 10 to 15 mg/kg intravenously every 6 to 24 hours, depending on age and renal clearance. Patients who had confirmed VRE infections were placed in a third arm of the study and received ZYVOX 10 mg/kg every 8 hours intravenously and/or orally. All patients were treated for a total of 10 to 28 days and could receive concomitant Gram-negative antibacterial drugs if clinically indicated. In the intent-to-treat (ITT) population, there were 206 patients randomized to linezolid and 102 patients randomized to vancomycin. The cure rates for ITT, MITT, and clinically evaluable patients are presented in Table 16. After the study was completed, 13 additional patients ranging from 4 days through 16 years of age were enrolled in an open-label extension of the VRE arm of the study. Table 17 provides clinical cure rates by pathogen for microbiologically evaluable patients including microbiologically evaluable patients with vancomycin-resistant Enterococcus faecium from the extension of this study.

Table 16. Cure Rates at the Test-of-Cure Visit for Intent-to-Treat, Modified Intent-to-Treat, and Clinically Evaluable Pediatric Patients for the Overall Population and by Select Baseline Diagnosis
 | ITT |  | MITT [MITT = ITT patients with an isolated Gram-positive pathogen at baseline] |  | Clinically Evaluable
Population | ZYVOX n/N (%) | Vancomycin n/N (%) | ZYVOX n/N (%) | Vancomycin n/N (%) | ZYVOX n/N (%) | Vancomycin n/N (%)
Any diagnosis | 150/186 (81) | 69/83 (83) | 86/108 (80) | 44/49 (90) | 106/117 (91) | 49/54 (91)
Complicated skin and skin structure infections | 61/72 (85) | 31/34 (91) | 37/43 (86) | 22/23 (96) | 46/49 (94) | 26/27 (96)
Nosocomial pneumonia | 13/18 (72) | 11/12 (92) | 5/6 (83) | 4/4 (100) | 7/7 (100) | 5/5 (100)

Table 17. Cure Rates at the Test-of-Cure Visit for Microbiologically Evaluable Pediatric Patients with Infections due to Gram-positive Pathogens
 | Microbiologically Evaluable
Pathogen | ZYVOX n/N (%) | Vancomycin n/N (%)
Vancomycin-resistant Enterococcus faecium | 6/8 (75) [Includes data from 7 patients enrolled in the open-label extension of this study.] | 0/0 (-)
Staphylococcus aureus | 36/38 (95) | 23/24 (96)
Methicillin-resistant S. aureus | 16/17 (94) | 9/9 (100)
Streptococcus pyogenes | 2/2 (100) | 1/2 (50)

16 HOW SUPPLIED/STORAGE AND HANDLING

16.1 Injection

ZYVOX I.V. Injection is available in single-dose, ready-to-use flexible plastic infusion bags in a foil laminate overwrap. The infusion bags and ports are not made with natural rubber latex. The infusion bags are available in the following package sizes:

200 mg/100 mL (2 mg/mL) linezolid × 10 | NDC 0009-5137-04
600 mg/300 mL (2 mg/mL) linezolid × 10 | NDC 0009-5140-04

16.2 Tablets

ZYVOX Tablets are available as follows:

600 mg (white, capsule-shaped, film-coated tablets debossed with "ZYV" on one side and "600" on the other)

20 tablets in HDPE bottle | NDC 0009-5138-02
Unit dose packages of 30 tablets | NDC 0009-5138-03

16.3 Oral Suspension

ZYVOX for Oral Suspension is available as a dry, white to off-white, orange-flavored granule/powder. When constituted as directed, each bottle will contain 150 mL of a suspension providing the equivalent of 100 mg of linezolid per each 5 mL. ZYVOX for Oral Suspension is supplied as follows:

100 mg/5 mL in 240 mL glass bottles | NDC 0009-5136-01
100 mg/5 mL in 240 mL glass bottles | NDC 0009-5136-04

16.4 Storage and Handling

Store at 25ºC (77ºF). Protect from light. Keep bottles tightly closed to protect from moisture. It is recommended that the infusion bags be kept in the overwrap until ready to use. Protect infusion bags from freezing.

17 PATIENT COUNSELING INFORMATION

Important Administration Instructions

Advise patients that ZYVOX may be taken with or without food.

Peripheral and Optic Neuropathy

Advise patients to inform their physician if they experience changes in vision while taking ZYVOX [see Warnings and Precautions (5.2)].

Serotonin Syndrome

Advise patients to inform their physician if taking serotonergic agents, including serotonin re-uptake inhibitors or other antidepressants and opioids [see Warnings and Precautions (5.3)].

Potential Interactions Producing Elevation of Blood Pressure

- Advise patients to inform their physician if they have a history of hypertension.
- Advise patients to avoid large quantities of foods or beverages with high tyramine content while taking ZYVOX. Foods high in tyramine content include those that may have undergone protein changes by aging, fermentation, pickling, or smoking to improve flavor, such as aged cheeses, fermented or air-dried meats, sauerkraut, soy sauce, tap beers, and red wines. The tyramine content of any protein-rich food may be increased if stored for long periods or improperly refrigerated.
- Advise patients to inform their physician if taking medications containing pseudoephedrine HCl or phenylpropanolamine HCl, such as cold remedies and decongestants [see Warnings and Precautions (5.6)].

Lactic Acidosis

Advise patients to inform their physician if they experience repeated episodes of nausea or vomiting while receiving ZYVOX [see Warnings and Precautions (5.7)].

Convulsions

Advise patients to inform their physician if they have a history of seizures or convulsions [see Warnings and Precautions (5.8)].

Rhabdomyolysis

Advise patients to inform their physician if they experience signs and symptoms of rhabdomyolysis including muscle pain, tenderness or weakness and dark urine [see Warnings and Precautions (5.9)].

Hypoglycemia

Advise patients to inform their physician if they have diabetes mellitus. Hypoglycemic reactions, such as diaphoresis and tremulousness, along with low blood glucose measurements may occur when treated with linezolid. If such reactions occur, patients should contact a physician or other health professional for proper treatment [see Warnings and Precautions (5.10)].

Hyponatremia and/or SIADH

Advise patients at risk for hyponatremia to inform their physician if they experience signs and symptoms of hyponatremia and/or SIADH, including confusion, somnolence, generalized weakness, and respiratory distress [see Warnings and Precautions (5.11)].

Phenylketonuria

Advise patients with phenylketonuria (PKU) that each 5 mL of the 100 mg/5 mL ZYVOX for Oral Suspension contains 20 mg phenylalanine. The other ZYVOX formulations do not contain phenylalanine. Phenylalanine can be harmful to patients with phenylketonuria. Contact your physician or pharmacist when prescribed with ZYVOX for Oral Suspension [see Warnings and Precautions (5.12)].

Antibacterial Resistance

Patients should be counseled that antibacterial drugs including ZYVOX should only be used to treat bacterial infections. They do not treat viral infections (e.g., the common cold). When ZYVOX is prescribed to treat a bacterial infection, patients should be told that although it is common to feel better early in the course of therapy, the medication should be taken exactly as directed. Skipping doses or not completing the full course of therapy may (1) decrease the effectiveness of the immediate treatment and (2) increase the likelihood that bacteria will develop resistance and will not be treatable by ZYVOX or other antibacterial drugs in the future.

Diarrhea

Diarrhea is a common problem caused by antibacterial drugs, which usually ends when the antibacterial drug is discontinued. Sometimes after starting treatment with antibacterial drugs, patients can develop watery and bloody stools (with or without stomach cramps and fever) even as late as two or more months after having taken the last dose of the antibacterial drug. If this occurs, patients should contact their physician as soon as possible [see Warnings and Precautions (5.5)].

Infertility

Advise male patients that ZYVOX may reversibly impair fertility [see Use in Specific Populations (8.3)].

This product's labeling may have been updated. For the most recent prescribing information, please visit www.pfizer.com.

LAB-0139-45.0

PRINCIPAL DISPLAY PANEL - 100 mL Bag Label

NDC 0009-5137-01
Rx only
ZYVOX®
(linezolid) injection

200 mg/100 mL
(2 mg/mL)

Store at 25°C (77°F); excursions
permitted to 15-30°C (59-86°F)
[see USP Controlled Room
Temperature]. Do not freeze.
Each mL contains:
linezolid
2 mg
dextrose, USP
50.24 mg
sodium citrate, USP
1.64 mg
citric acid, USP
0.85 mg
water for injection, USP
qs
pH adjusted to 4.8 with sodium
hydroxide or hydrochloric acid.
Sterile and nonpyrogenic. Single
dose container.
Do not add supplementary
medication. Do not use in
series connections.

For intravenous
administration
Check for leaks by
squeezing container.
If leaks are found, discard,
as sterility may be impaired.
Check linezolid solution for
clarity; it may exhibit a
yellow color that
intensifies over
time, with no adverse
effect on potency.
DOSAGE AND USE:
See accompanying
prescribing information.
DISCARD UNUSED
PORTION. The Infusion
Bags and Ports are Not
Made With Natural
Rubber Latex.
MADE IN SINGAPORE

freeflex

Pfizer
Hospital

7
OTHER

Distributed by
Pharmacia &
Upjohn Co. LLC
A subsidiary of
Pfizer Inc
NY, NY 10017

1234567890
FUU 0701 01-68-26-019F

LOT
EXP

PRINCIPAL DISPLAY PANEL - 100 mL Bag Overwrap Label

NDC 0009-5137-01
Rx only
ZYVOX®
(linezolid) injection

200 mg/100 mL
(2 mg/mL)

Store at 25°C (77°F);
excursions permitted to
15-30°C (59-86°F) [see USP
Controlled Room
Temperature]. Do not freeze.
Each mL contains:
linezolid
2 mg
dextrose, USP
50.24 mg
sodium citrate, USP
1.64 mg
citric acid, USP
0.85 mg
water for injection, USP
qs
pH adjusted to 4.8 with sodium
hydroxide or hydrochloric acid.
Sterile and nonpyrogenic.
Single dose container.

Do not use in series
connections.
For intravenous administration
Check for leaks by squeezing
container. If leaks are found,
discard, as sterility may be
impaired.
Linezolid is sensitive to light.
Retain overwrap prior to use.
DOSAGE AND USE: See
accompanying prescribing
information.
DISCARD UNUSED PORTION.
The Infusion Bags and Ports
are Not Made With Natural
Rubber Latex.
MADE IN SINGAPORE

Pfizer
Hospital

7
OTHER

Distributed by
Pharmacia & Upjohn Co. LLC
A subsidiary of Pfizer Inc.
New York, NY 10017

FUU 0701 01-78-26-019G

LOT
EXP

PRINCIPAL DISPLAY PANEL - 100 mL Bag Box Label

NDC 0009-5137-04
Contains 10 of NDC 0009-5137-01
QUANTITY: 1 (10 IV BAGS X 100 mL)

ZYVOX®
(linezolid) injection
200 mg/100mL (2 mg/mL)

RX ONLY
STORE AT 25°C (77°F); EXCURSIONS PERMITTED TO 15-30°C (59-86°F)
[SEE USP CONTROLLED ROOM TEMPERATURE]. DO NOT FREEZE.
DISCARD UNUSED PORTION. The Infusion Bags and Ports are Not Made With Natural Rubber Latex.

Distributed by
Pharmacia & Upjohn Company LLC
A subsidiary of Pfizer Inc.
New York, NY 10017
MADE IN SINGAPORE

EXP YYYY-MM
LOT 00000000
QTY: 01

04.30.034

FUU 0701 01-88-26-019L

PRINCIPAL DISPLAY PANEL - 300 mL Bag Label

NDC 0009-5140-01
Rx only
ZYVOX®
(linezolid) injection

600 mg/300 mL
(2 mg/mL)

Store at 25°C (77°F); excursions
permitted to 15-30°C (59-86°F)
[see USP Controlled Room
Temperature].
Do not freeze.
Each mL contains:
linezolid
2 mg
dextrose, USP
50.24 mg
sodium citrate, USP
1.64 mg
citric acid, USP
0.85 mg
water for injection, USP
qs
pH adjusted to 4.8 with sodium
hydroxide or hydrochloric acid.
Sterile and nonpyrogenic.
Single dose container.

Do not add supplementary
medication. Do not use in
series connections.
For intravenous administration
Check for leaks by squeezing
container. If leaks are found,
discard, as sterility may be
impaired.
Check linezolid solution for
clarity; it may exhibit a yellow
color that intensifies over time,
with no adverse effect on
potency.
DOSAGE AND USE:
See accompanying
prescribing information.
DISCARD UNUSED PORTION.
The Infusion Bags and Ports are
Not Made With Natural Rubber
Latex.
MADE IN SINGAPORE

Pfizer
Hospital

7
OTHER

Distributed by
Pharmacia & Upjohn Co. LLC
A subsidiary of Pfizer Inc.
New York, NY 10001

freeflex

1234567890
FUU 0703 01-68-26-020G

LOT
EXP

PRINCIPAL DISPLAY PANEL - 300 mL Bag Overwrap Label

NDC 0009-5140-01
Rx only
ZYVOX®
(linezolid) injection

600 mg/300 mL
(2 mg/mL)

Store at 25°C (77°F); excursions
permitted to 15-30°C (59-86°F)
[see USP Controlled Room
Temperature]. Do not freeze.
Each mL contains:
linezolid
2 mg
dextrose, USP
50.24 mg
sodium citrate, USP
1.64 mg
citric acid, USP
0.85 mg
water for injection, USP
qs
pH adjusted to 4.8 with sodium
hydroxide or hydrochloric acid.
Sterile and nonpyrogenic.
Single dose container.
Do not use in series
connections.

For intravenous administration
Check for leaks by squeezing
container. If leaks are found,
discard, as sterility may be
impaired.
Linezolid is sensitive to light.
Retain overwrap prior to use.
DOSAGE AND USE: See
accompanying prescribing
information.
DISCARD UNUSED PORTION.
The Infusion Bags and Ports
are Not Made With Natural
Rubber Latex.
MADE IN SINGAPORE

Pfizer
Hospital

Distributed by
Pharmacia & Upjohn Company LLC
A subsidiary of Pfizer Inc.
New York, NY 10001

7
OTHER

FUU 0703 01-78-26-020H

LOT
YYMDDU00
EXP
YYYY-MM

PRINCIPAL DISPLAY PANEL - 300 mL Bag Box Label

NDC 0009-5140-04
Contains 10 of NDC 0009-5140-01
QUANTITY: 1 (10 IV BAGS X 300 mL)

ZYVOX®
(linezolid) injection
600 mg/300mL (2 mg/mL)

RX ONLY
STORE AT 25°C (77°F); EXCURSIONS PERMITTED TO 15-30°C (59-86°F)
[SEE USP CONTROLLED ROOM TEMPERATURE]. DO NOT FREEZE.
DISCARD UNUSED PORTION. The Infusion Bags and Ports are Not Made With Natural Rubber Latex.

Distributed by
Pharmacia & Upjohn Company LLC
A subsidiary of Pfizer Inc.
New York, NY 10001
MADE IN SINGAPORE

EXP YYYY-MM
LOT 00000000
QTY: 01

04.30.034

FUU 0703 01-88-26-020M

PRINCIPAL DISPLAY PANEL - 150 mL Bottle Label

NDC 0009-5136-01

150 mL (when constituted)
Rx only

ZYVOX®

(linezolid) for
oral suspension

100 mg/5 mL

Pfizer
Distributed by
Pharmacia & Upjohn Co
Division of Pfizer Inc, NY, NY 10017

PRINCIPAL DISPLAY PANEL - 150 mL Bottle Carton

NDC 0009-5136-01
150 mL (when constituted)
Rx only

ZYVOX®

(linezolid) for
oral suspension

100 mg/5 mL

Pfizer
Distributed by
Pharmacia & Upjohn Co
Division of Pfizer Inc, NY, NY 10017

PRINCIPAL DISPLAY PANEL - 600 mg Tablet Bottle Label - NDC 0009-5138-02

Pfizer
NDC 0009-5138-02

Zyvox®
(linezolid) tablets

600 mg

20 Tablets
Rx only

PRINCIPAL DISPLAY PANEL - 600 mg Tablet Blister Pack - NDC 0009-5138-03

Zyvox®
(linezolid) tablets

600 mg

Distributed by
Pharmacia & Upjohn Co. LLC
A sub. of Pfizer Inc., NY, NY 10001
75098987

EXP &
LOT AREA

PRINCIPAL DISPLAY PANEL - 600 mg Tablet Blister Pack Carton - NDC 0009-5138-03

UNIT DOSE

Pfizer
NDC 0009-5138-03

Zyvox®
(linezolid) tablets

600 mg

For in-institution use only

30 Tablets
Rx only